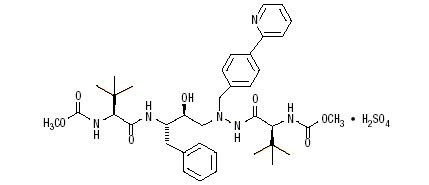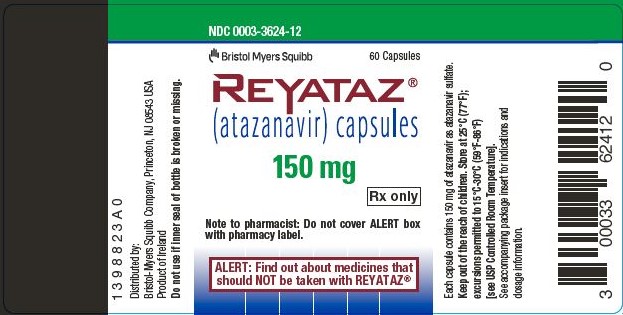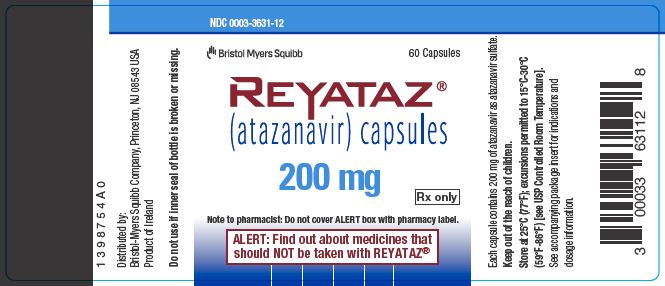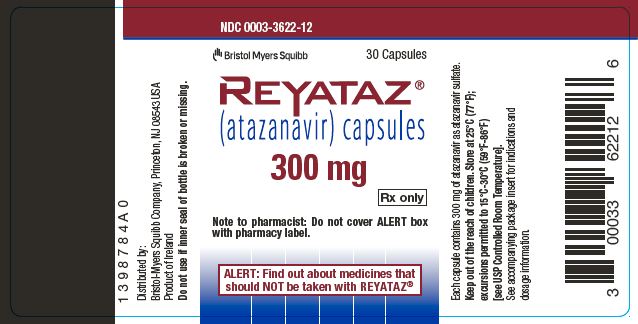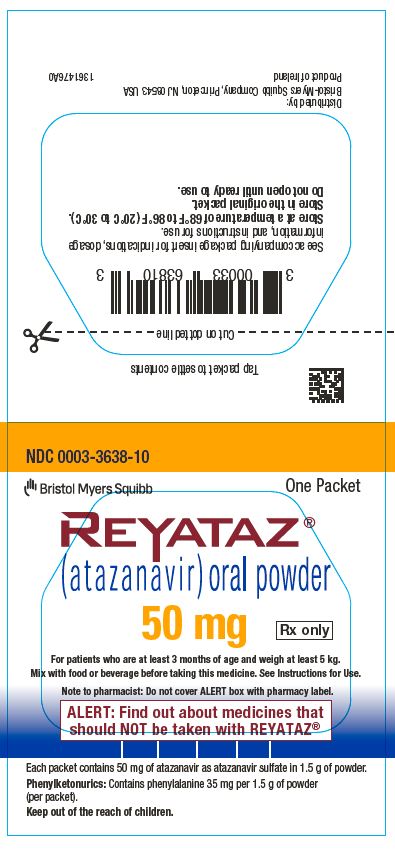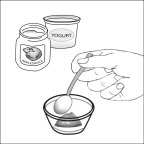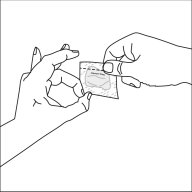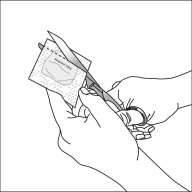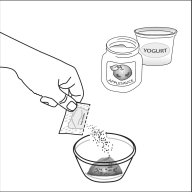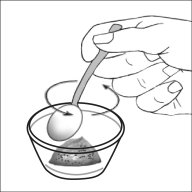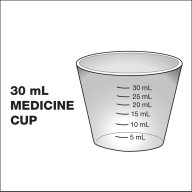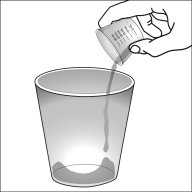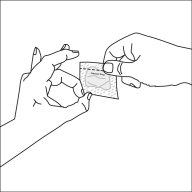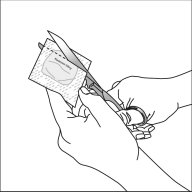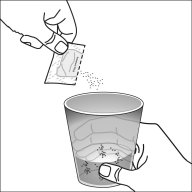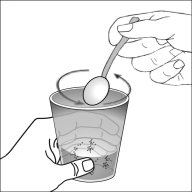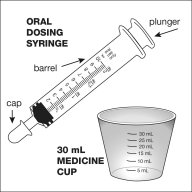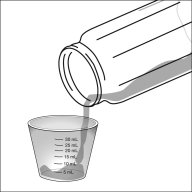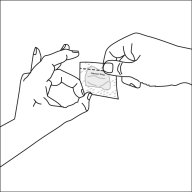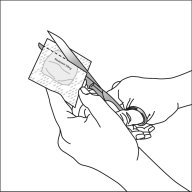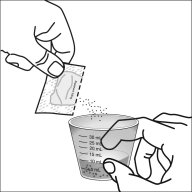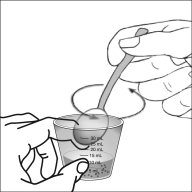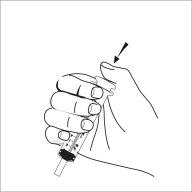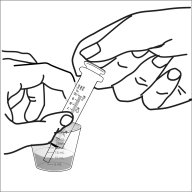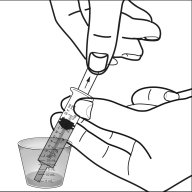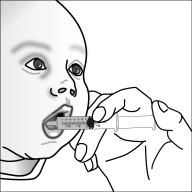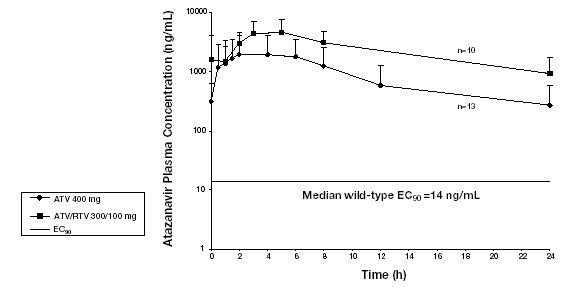 DRUG LABEL: REYATAZ
NDC: 0003-3624 | Form: CAPSULE, GELATIN COATED
Manufacturer: E.R. Squibb & Sons, L.L.C.
Category: prescription | Type: HUMAN PRESCRIPTION DRUG LABEL
Date: 20241205

ACTIVE INGREDIENTS: ATAZANAVIR SULFATE 150 mg/1 1
INACTIVE INGREDIENTS: CROSPOVIDONE (120 .MU.M); LACTOSE MONOHYDRATE; MAGNESIUM STEARATE; GELATIN, UNSPECIFIED; FD&C BLUE NO. 2; TITANIUM DIOXIDE; FERRIC OXIDE RED; FERRIC OXIDE YELLOW; ISOPROPYL ALCOHOL; AMMONIA; PROPYLENE GLYCOL; BUTYL ALCOHOL; ALCOHOL; FERROSOFERRIC OXIDE; SHELLAC

HIGHLIGHTS OF PRESCRIBING INFORMATION

These highlights do not include all the information needed to use REYATAZ safely and effectively. See full prescribing information for REYATAZ.
REYATAZ® (atazanavir) capsules, for oral use
REYATAZ® (atazanavir) oral powder
Initial U.S. Approval: 2003

RECENT MAJOR CHANGES

Contraindications (4) | 12/2024

1 INDICATIONS AND USAGE

REYATAZ is a protease inhibitor indicated for use in combination with other antiretroviral agents for the treatment of HIV-1 infection in adults and in pediatric patients 3 months and older weighing at least 5 kg. (1)

2 DOSAGE AND ADMINISTRATION

- Pretreatment testing: Renal laboratory testing should be performed in all patients prior to initiation of REYATAZ and continued during treatment with REYATAZ. Hepatic testing should be performed in patients with underlying liver disease prior to initiation of REYATAZ and continued during treatment with REYATAZ. (2.2)
- Treatment-naive adults: REYATAZ 300 mg with ritonavir 100 mg once daily with food or REYATAZ 400 mg once daily with food. (2.3)
- Treatment-experienced adults: REYATAZ 300 mg with ritonavir 100 mg once daily with food. (2.3)
- Pediatric patients: REYATAZ capsule dosage is based on body weight not to exceed the adult dose and must be taken with food. (2.4)
- REYATAZ oral powder: Must be taken with ritonavir and food and should not be used in pediatric patients who weigh less than 5 kg. (2.5)
- Pregnancy: REYATAZ 300 mg with ritonavir 100 mg once daily with food, with dosing modifications for some concomitant medications. (2.6)
- Dosing modifications: may be required for concomitant therapy (2.3, 2.4, 2.5, 2.6), renal impairment (2.7), and hepatic impairment. (2.8)

3 DOSAGE FORMS AND STRENGTHS

- Capsules: 200 mg, 300 mg. (3, 16)
- Oral powder: 50 mg packet. (3, 16)

4 CONTRAINDICATIONS

- In patients with previously demonstrated hypersensitivity (eg, Stevens-Johnson syndrome, erythema multiforme, or toxic skin eruptions) to any of the components of REYATAZ. (4)
- Coadministration with drugs that are strong inducers of CYP3A, due to the potential for loss of therapeutic effect and development of resistance. (4)
- Coadministration with drugs that are highly dependent on CYP3A or UGT1A1 for clearance, and for which elevated plasma concentrations of the interacting drugs are associated with serious and/or life-threatening events. (4)

5 WARNINGS AND PRECAUTIONS

- Cardiac conduction abnormalities: PR interval prolongation may occur in some patients. ECG monitoring should be considered in patients with preexisting conduction system disease or when administered with other drugs that may prolong the PR interval. (5.1, 7.3, 12.2, 17)
- Severe Skin Reactions: Discontinue if severe rash develops. (5.2, 17)
- Hyperbilirubinemia: Most patients experience asymptomatic increases in indirect bilirubin, which is reversible upon discontinuation. Do not dose reduce. If a concomitant transaminase increase occurs, evaluate for alternative etiologies. (5.8)
- Phenylketonuria: REYATAZ oral powder contains phenylalanine which can be harmful to patients with phenylketonuria. (5.3)
- Hepatotoxicity: Patients with hepatitis B or C virus are at risk of increased transaminases or hepatic decompensation. Monitor hepatic laboratory tests prior to therapy and during treatment. (2.8, 5.4, 8.8)
- Chronic kidney disease has been reported during postmarketing surveillance in patients with HIV-1 treated with atazanavir, with or without ritonavir. Consider alternatives in patients at high risk for renal disease or with preexisting renal disease. Monitor renal laboratory tests prior to therapy and during treatment. Consider discontinuation of REYATAZ in patients with progressive renal disease. (5.5)
- Nephrolithiasis and cholelithiasis have been reported. Consider temporary interruption or discontinuation. (5.6)
- The concomitant use of REYATAZ with ritonavir and certain other medications may result in known or potentially significant drug interactions. Consult the full prescribing information prior to and during treatment for potential drug interactions. (5.7, 7.3)
- Patients receiving REYATAZ may develop new onset or exacerbations of diabetes mellitus/hyperglycemia (5.9), immune reconstitution syndrome (5.10), and redistribution/accumulation of body fat. (5.11)
- Hemophilia: Spontaneous bleeding may occur, and additional factor VIII may be required. (5.12)

6 ADVERSE REACTIONS

Most common adverse reactions (≥2%) are nausea, jaundice/scleral icterus, rash, headache, abdominal pain, vomiting, insomnia, peripheral neurologic symptoms, dizziness, myalgia, diarrhea, depression, and fever. (6.1)

To report SUSPECTED ADVERSE REACTIONS, contact Bristol-Myers Squibb at 1-800-721-5072 or FDA at 1-800-FDA-1088 or www.fda.gov/medwatch.

7 DRUG INTERACTIONS

Coadministration of REYATAZ can alter the concentration of other drugs and other drugs may alter the concentration of atazanavir. The potential drug-drug interactions must be considered prior to and during therapy. (4, 7, 12.3)

8 USE IN SPECIFIC POPULATIONS

- Pregnancy: Available human and animal data suggest that atazanavir does not increase the risk of major birth defects overall compared to the background rate. (8.1)
- Hepatitis B or C co-infection: Monitor liver enzymes. (5.4, 6.1)
- Renal impairment: REYATAZ is not recommended for use in treatment-experienced patients with end-stage renal disease managed with hemodialysis. (2.7, 8.7)
- Hepatic impairment: REYATAZ is not recommended in patients with severe hepatic impairment. REYATAZ with ritonavir is not recommended in patients with any degree of hepatic impairment. (2.8, 8.8)

FULL PRESCRIBING INFORMATION

1 INDICATIONS AND USAGE

REYATAZ® is indicated in combination with other antiretroviral agents for the treatment of HIV-1 infection in adults and in pediatric patients 3 months and older weighing at least 5 kg.

Limitations of Use:

- REYATAZ is not recommended for use in pediatric patients below the age of 3 months due to the risk of kernicterus [see Use in Specific Populations (8.4)].
- Use of REYATAZ with ritonavir in treatment-experienced patients should be guided by the number of baseline primary protease inhibitor resistance substitutions [see Microbiology (12.4)].

2 DOSAGE AND ADMINISTRATION

2.1 Overview

- REYATAZ capsules and oral powder must be taken with food.
- Do not open the capsules.
- The recommended oral dosage of REYATAZ depends on the treatment history of the patient and the use of other coadministered drugs. When coadministered with H2-receptor antagonists or proton-pump inhibitors, dose separation may be required [see Dosage and Administration (2.3, 2.4, 2.5, and 2.6) and Drug Interactions (7)].
- REYATAZ capsules without ritonavir are not recommended for treatment-experienced adult or pediatric patients with prior virologic failure [see Clinical Studies (14)].
- REYATAZ oral powder must be taken with ritonavir and is not recommended for use in children who weigh less than 5 kg [see Dosage and Administration (2.5)].
- Efficacy and safety of REYATAZ with ritonavir when ritonavir is administered in doses greater than 100 mg once daily have not been established. The use of higher ritonavir doses may alter the safety profile of atazanavir (cardiac effects, hyperbilirubinemia) and, therefore, is not recommended. Prescribers should consult the complete prescribing information for ritonavir when using ritonavir.

2.2 Testing Prior to Initiation and During Treatment with REYATAZ

Renal laboratory testing should be performed in all patients prior to initiation of REYATAZ and continued during treatment with REYATAZ. Renal laboratory testing should include serum creatinine, estimated creatinine clearance, and urinalysis with microscopic examination [see Warnings and Precautions (5.5, 5.6)].

Hepatic laboratory testing should be performed in patients with underlying liver disease prior to initiation of REYATAZ and continued during treatment with REYATAZ [see Warnings and Precautions (5.4)].

2.3 Dosage of REYATAZ in Adult Patients

Table 1 displays the recommended dosage of REYATAZ capsules in treatment-naive and treatment-experienced adults. Table 1 also displays recommended dosage of REYATAZ and ritonavir when given concomitantly with other antiretroviral drugs and H2-receptor antagonists (H2RA). Ritonavir is required with several REYATAZ dosage regimens (see the ritonavir complete prescribing information about the safe and effective use of ritonavir). The use of REYATAZ in treatment-experienced adult patients without ritonavir is not recommended.

Table 1: Recommended REYATAZ and Ritonavir Dosage in Adultsa,b
 | REYATAZ Once Daily Dosage | Ritonavir Once Daily Dosage
Treatment-Naive Adult Patients
recommended regimen | 300 mg | 100 mg
unable to tolerate ritonavir | 400 mg | N/A
in combination with efavirenz | 400 mg | 100 mg
Treatment-Experienced Adult Patients
recommended regimen | 300 mg | 100 mg
in combination with both H2RA and tenofovir DF | 400 mg | 100 mg
a See Drug Interactions (7) for instructions concerning coadministration of acid-reducing medications (eg, H2RA or proton pump inhibitors [PPIs]), and other antiretroviral drugs (eg, efavirenz, tenofovir DF, and didanosine).
b For adult patients who cannot swallow the capsules, REYATAZ oral powder is taken once daily with food at the same recommended adult dosage as the capsules along with ritonavir.

2.4 Dosage of REYATAZ Capsules in Pediatric Patients

The recommended daily dosage of REYATAZ capsules and ritonavir in pediatric patients (6 years of age to less than 18 years of age) is based on body weight (see Table 2).

Table 2: Recommended Dosage of REYATAZ Capsules and Ritonavir in Pediatric Patients (6 to less than 18 years of age)a,b
Body weight | REYATAZ Daily Dosage | Ritonavir Daily Dosage
Treatment-Naive and Treatment-Experiencedc
Less than 15 kg | Capsules not recommended | N/A
At least 15 kg to less than 35 kg | 200 mg | 100 mg
At least 35 kg | 300 mg | 100 mg
Treatment-Naive, at least 13 years old and cannot tolerate ritonavir
At least 40 kg | 400 mg | N/A
a Administer REYATAZ capsules and ritonavir simultaneously with food.
b The same recommendations regarding the timing and maximum doses of concomitant PPIs and H2RAs in adults also apply to pediatric patients. See Drug Interactions (7) for instructions concerning coadministration of acid-reducing medications (eg, H2RA or PPIs), and other antiretroviral drugs (eg, efavirenz, tenofovir DF, and didanosine).
c In treatment-experienced patients, REYATAZ capsules must be administered with ritonavir.

When transitioning between formulations, a change in dose may be needed. Consult the dosing table for the specific formulation.

2.5 Dosage and Administration of REYATAZ Oral Powder in Pediatric Patients

REYATAZ oral powder is for use in treatment-naive or treatment-experienced pediatric patients who are at least 3 months of age and weighing at least 5 kg. REYATAZ oral powder must be mixed with food or a beverage for administration and ritonavir must be given immediately afterwards. Table 3 displays the recommended dosage of REYATAZ oral powder and ritonavir.

Table 3: Recommended Dosage of REYATAZ Oral Powder and Ritonavir in Pediatric Patients (at least 3 months of age and weighing at least 5 kg)a,b
Body Weight | Daily Dosage of REYATAZ Oral Powder | Daily Dosage of Ritonavir Oral Solution
5 kg to less than 15 kg | 200 mg (4 packets)c,d | 80 mg
15 kg to less than 25 kg | 250 mg (5 packets)d | 80 mg
a The same recommendations regarding the timing and maximum doses of concomitant PPIs and H2RAs in adults also apply to pediatric patients. See Drug Interactions (7) for instructions concerning coadministration of acid-reducing medications (eg, H2RA or PPIs), and other antiretroviral drugs (eg, efavirenz, tenofovir DF, and didanosine).
b For pediatric patients at least 25 kg who cannot swallow REYATAZ capsules, 300 mg (6 packets) REYATAZ oral powder is taken once daily with food along with 100 mg ritonavir.
c Only patients weighing 5 to less than 10 kg who do not tolerate the 200 mg (4 packets) dose of REYATAZ oral powder and have not previously taken an HIV protease inhibitor, may take 150 mg (3 packets) REYATAZ oral powder with close HIV viral load monitoring.
d Each packet contains 50 mg of REYATAZ.

When transitioning between formulations, a change in dose may be needed. Consult the dosing table for the specific formulation.

Instructions for Mixing REYATAZ Oral Powder [see FDA-approved Instructions for Use]

- Determine the number of packets (3, 4, 5 or 6 packets) that are needed.
- Prior to mixing, tap the packet to settle the powder.
- It is preferable to mix REYATAZ oral powder with food such as applesauce or yogurt. Mixing REYATAZ oral powder with a beverage (milk, infant formula, or water) may be used for infants who can drink from a cup. For young infants (less than 6 months) who cannot eat solid food or drink from a cup, REYATAZ oral powder should be mixed with infant formula and given using an oral dosing syringe. Administration of REYATAZ and infant formula using an infant bottle is not recommended because full dose may not be delivered.
- Use a clean pair of scissors to cut each packet along the dotted line.
- Mixing with food: Using a spoon, mix the recommended number of REYATAZ oral powder packets with a minimum of one tablespoon of food (such as applesauce or yogurt). Feed the mixture to the infant or young child. Add an additional one tablespoon of food to the small container, mix, and feed the child the residual mixture.
- Mixing with a beverage such as milk or water in a small drinking cup: Using a spoon, mix the recommended number of REYATAZ oral powder packets with a minimum of 30 mL of the beverage. Have the child drink the mixture. Add an additional 15 mL more of beverage to the drinking cup, mix, and have the child drink the residual mixture. If water is used, food should also be taken at the same time.
- Mixing with liquid infant formula using an oral dosing syringe and a small medicine cup: Using a spoon, mix the recommended number of REYATAZ oral powder packets with 10 mL of prepared liquid infant formula. Draw up the full amount of the mixture into an oral syringe and administer into either right or left inner cheek of infant. Pour another 10 mL of formula into the medicine cup to rinse off remaining REYATAZ oral powder in cup. Draw up residual mixture into the syringe and administer into either right or left inner cheek of infant.
- Administer ritonavir immediately following REYATAZ powder administration.
- Administer the entire dosage of REYATAZ oral powder (mixed in the food or beverage) within one hour of preparation [may leave the mixture at a temperature of 68°F to 86°F (20°C to 30°C) for up to one hour]. Ensure that the patient eats or drinks all the food or beverage that contains the powder. Additional food may be given after consumption of the entire mixture.

2.6 Dosage Adjustments in Pregnant Patients

Table 4 includes the recommended dosage of REYATAZ capsules and ritonavir in treatment-naive and treatment-experienced pregnant patients. In these patients, REYATAZ must be administered with ritonavir. There are no dosage adjustments for postpartum patients (see Table 1 for the recommended REYATAZ dosage in adults) [see Use in Specific Populations (8.1)].

Table 4: Recommended Dosage of REYATAZ and Ritonavir in Pregnant Patientsa
 | REYATAZ Once Daily Dosage | Ritonavir Once Daily Dosage
Treatment-Naive and Treatment-Experienced
Recommended Regimen | 300 mg | 100 mg
Treatment-Experienced During the Second or Third Trimester When Coadministered with either H2RA or Tenofovir DFb
In combination with EITHER H2RA OR tenofovir DF | 400 mg | 100 mg
a See Drug Interactions (7) for instructions concerning coadministration of acid-reducing medications (eg, H2RA or PPIs), and other antiretroviral drugs (eg, efavirenz, tenofovir DF, and didanosine).
b REYATAZ is not recommended for treatment-experienced pregnant patients during the second and third trimester taking REYATAZ with BOTH tenofovir DF and H2RA.

2.7 Dosage in Patients with Renal Impairment

For patients with renal impairment, including those with severe renal impairment who are not managed with hemodialysis, no dose adjustment is required for REYATAZ. Treatment-naive patients with end-stage renal disease managed with hemodialysis should receive REYATAZ 300 mg with ritonavir 100 mg. REYATAZ is not recommended in treatment-experienced patients with HIV-1 who have end-stage renal disease managed with hemodialysis [see Use in Specific Populations (8.7)].

2.8 Dosage Adjustments in Patients with Hepatic Impairment

Table 5 displays the recommended REYATAZ dosage in treatment-naive patients with hepatic impairment. The use of REYATAZ in patients with severe hepatic impairment (Child-Pugh Class C) is not recommended. The coadministration of REYATAZ with ritonavir in patients with any degree of hepatic impairment is not recommended.

Table 5: Recommended Dosage of REYATAZ Capsules in Treatment-Naive Adults with Hepatic Impairment
 | REYATAZ Once Daily Dosage
Mild hepatic impairment (Child-Pugh Class A) | 400 mg
Moderate hepatic impairment (Child-Pugh Class B) | 300 mg
Severe hepatic impairment (Child-Pugh Class C) | REYATAZ with or without ritonavir is not recommended

3 DOSAGE FORMS AND STRENGTHS

REYATAZ Capsules:

- 200 mg capsule with blue cap and blue body, printed with white ink “BMS 200 mg” on the cap and with white ink “3631” on the body.
- 300 mg capsule with red cap and blue body, printed with white ink “BMS 300 mg” on the cap and with white ink “3622” on the body.

REYATAZ Oral Powder:

- 50 mg of atazanavir as an oral powder in a packet.

4 CONTRAINDICATIONS

REYATAZ is contraindicated:

- in patients with previously demonstrated clinically significant hypersensitivity (eg, Stevens-Johnson syndrome, erythema multiforme, or toxic skin eruptions) to any of the components of REYATAZ capsules or REYATAZ oral powder [see Warnings and Precautions (5.2)].
- when coadministered with drugs that are highly dependent on CYP3A or UGT1A1 for clearance, and for which elevated plasma concentrations of the interacting drugs are associated with serious and/or life-threatening events (see Table 6).
- when coadministered with drugs that are strong inducers of CYP3A due to the potential for loss of therapeutic effect and development of resistance.

Coadministration is contraindicated with, but not limited to, the following drugs listed in Table 6:

Table 6: Drugs Contraindicated with REYATAZ (Information in the table applies to REYATAZ with or without ritonavir, unless otherwise indicated)
Drug Class | Drugs within class that are contraindicated with REYATAZ
Alpha 1-adrenoreceptor antagonist | Alfuzosin
Anticonvulsants | Carbamazepine, phenobarbital, phenytoin
Antiarrhythmics | Amiodarone (with ritonavir), quinidine (with ritonavir)
Antimycobacterials | Rifampin
Antineoplastics | Apalutamide, encorafenib, irinotecan, ivosidenib
Antipsychotics | Lurasidone (with ritonavir), pimozide
Benzodiazepines | Orally administered midazolama, triazolam
Ergot Derivatives | Dihydroergotamine, ergonovine, ergotamine, methylergonovine
GI Motility Agent | Cisapride
Hepatitis C Direct-Acting Antivirals | Elbasvir/grazoprevir; glecaprevir/pibrentasvir
Herbal Products | St. John’s wort (Hypericum perforatum)
Lipid-Modifying Agents: | Lomitapide, lovastatin, simvastatin
Phosphodiesterase-5 (PDE-5) Inhibitor | Sildenafilb when dosed as REVATIO® for the treatment of pulmonary arterial hypertension
Protease Inhibitors | Indinavir
Non-nucleoside Reverse Transcriptase Inhibitors | Nevirapine
a See Drug Interactions, Table 16 (7) for parenterally administered midazolam.
b See Drug Interactions, Table 16 (7) for sildenafil when dosed as VIAGRA® for erectile dysfunction.

5 WARNINGS AND PRECAUTIONS

5.1 Cardiac Conduction Abnormalities

REYATAZ has been shown to prolong the PR interval of the electrocardiogram in some study participants. In healthy participants and in participants with HIV-1 treated with atazanavir, abnormalities in atrioventricular (AV) conduction were asymptomatic and generally limited to first-degree AV block. There have been reports of second-degree AV block and other conduction abnormalities [see Adverse Reactions (6.2) and Overdosage (10)]. In clinical trials that included electrocardiograms, asymptomatic first-degree AV block was observed in 5.9% of atazanavir-treated participants (n=920), 5.2% of lopinavir/ritonavir-treated participants (n=252), 10.4% of nelfinavir-treated participants (n=48), and 3.0% of efavirenz-treated participants (n=329). In Study AI424-045, asymptomatic first-degree AV block was observed in 5% (6/118) of atazanavir with ritonavir-treated participants and 5% (6/116) of lopinavir/ritonavir-treated participants who had on-study electrocardiogram measurements. Because of limited clinical experience in those with preexisting conduction system disease (eg, marked first-degree AV block or second- or third-degree AV block), ECG monitoring should be considered in these patients [see Clinical Pharmacology (12.2)].

5.2 Severe Skin Reactions

In controlled clinical trials, rash (all grades, regardless of causality) occurred in approximately 20% of participants with HIV-1 treated with REYATAZ. The median time to onset of rash in clinical studies was 7.3 weeks and the median duration of rash was 1.4 weeks. Rashes were generally mild-to-moderate maculopapular skin eruptions. Treatment-emergent adverse reactions of moderate or severe rash (occurring at a rate of ≥2%) are presented for the individual clinical studies [see Adverse Reactions (6.1)]. Dosing with REYATAZ was often continued without interruption in patients who developed rash. The discontinuation rate for rash in clinical trials was <1%. Cases of Stevens-Johnson syndrome, erythema multiforme, and toxic skin eruptions, including drug rash, eosinophilia, and systemic symptoms (DRESS) syndrome, have been reported in patients receiving REYATAZ [see Contraindications (4) and Adverse Reactions (6.1)]. REYATAZ should be discontinued if severe rash develops.

5.3 Patients with Phenylketonuria

Phenylalanine can be harmful to patients with phenylketonuria (PKU). REYATAZ oral powder contains phenylalanine (a component of aspartame). Each packet of REYATAZ oral powder contains 35 mg of phenylalanine. REYATAZ capsules do not contain phenylalanine.

5.4 Hepatotoxicity

Patients with underlying hepatitis B or C virus or marked elevations in transaminases before treatment may be at increased risk for developing further transaminase elevations or hepatic decompensation. In these patients, hepatic laboratory testing should be conducted prior to initiating therapy with REYATAZ and during treatment [see Dosage and Administration (2.2), Adverse Reactions (6.1), and Use in Specific Populations (8.8)].

5.5 Chronic Kidney Disease

Chronic kidney disease in patients with HIV-1 treated with atazanavir, with or without ritonavir, has been reported during postmarketing surveillance. Reports included biopsy-proven cases of granulomatous interstitial nephritis associated with the deposition of atazanavir drug crystals in the renal parenchyma. Consider alternatives to REYATAZ in patients at high risk for renal disease or with preexisting renal disease. Renal laboratory testing (including serum creatinine, estimated creatinine clearance, and urinalysis with microscopic examination) should be conducted in all patients prior to initiating therapy with REYATAZ and continued during treatment with REYATAZ. Expert consultation is advised for patients who have confirmed renal laboratory abnormalities while taking REYATAZ. In patients with progressive kidney disease, discontinuation of REYATAZ may be considered [see Dosage and Administration (2.2 and 2.7) and Adverse Reactions (6.2)].

5.6 Nephrolithiasis and Cholelithiasis

Cases of nephrolithiasis and/or cholelithiasis have been reported during postmarketing surveillance in patients with HIV-1 receiving REYATAZ therapy. Some patients required hospitalization for additional management, and some had complications. Because these events were reported voluntarily during clinical practice, estimates of frequency cannot be made. If signs or symptoms of nephrolithiasis and/or cholelithiasis occur, temporary interruption or discontinuation of therapy may be considered [see Adverse Reactions (6.2)].

5.7 Risk of Serious Adverse Reactions Due to Drug Interactions

Initiation of REYATAZ with ritonavir, a CYP3A inhibitor, in patients receiving medications metabolized by CYP3A or initiation of medications metabolized by CYP3A in patients already receiving REYATAZ with ritonavir, may increase plasma concentrations of medications metabolized by CYP3A. Initiation of medications that inhibit or induce CYP3A may increase or decrease concentrations of REYATAZ with ritonavir, respectively. These interactions may lead to:

- clinically significant adverse reactions potentially leading to severe, life-threatening, or fatal events from greater exposures of concomitant medications.
- clinically significant adverse reactions from greater exposures of REYATAZ with ritonavir.
- loss of therapeutic effect (virologic response) of REYATAZ with ritonavir and possible development of resistance.

See Table 16 for steps to prevent or manage these possible and known significant drug interactions, including dosing recommendations [see Drug Interactions (7)]. Consider the potential for drug interactions prior to and during therapy containing REYATAZ with ritonavir; and monitor for the adverse reactions associated with concomitant medications [see Contraindications (4) and Drug Interactions (7)].

5.8 Hyperbilirubinemia

Most patients taking REYATAZ experience asymptomatic elevations in indirect (unconjugated) bilirubin related to inhibition of UDP-glucuronosyl transferase (UGT). This hyperbilirubinemia is reversible upon discontinuation of REYATAZ. Hepatic transaminase elevations that occur with hyperbilirubinemia should be evaluated for alternative etiologies. No long-term safety data are available for patients experiencing persistent elevations in total bilirubin >5 times the upper limit of normal (ULN). Alternative antiretroviral therapy to REYATAZ may be considered if jaundice or scleral icterus associated with bilirubin elevations presents cosmetic concerns for patients. Dose reduction of atazanavir is not recommended since long-term efficacy of reduced doses has not been established [see Adverse Reactions (6.1)].

5.9 Diabetes Mellitus/Hyperglycemia

New-onset diabetes mellitus, exacerbation of preexisting diabetes mellitus, and hyperglycemia have been reported during postmarketing surveillance in patients with HIV-1 receiving protease inhibitor therapy. Some patients required either initiation or dose adjustments of insulin or oral hypoglycemic agents for treatment of these events. In some cases, diabetic ketoacidosis has occurred. In those patients who discontinued protease inhibitor therapy, hyperglycemia persisted in some cases. Because these events have been reported voluntarily during clinical practice, estimates of frequency cannot be made and a causal relationship between protease inhibitor therapy and these events has not been established [see Adverse Reactions (6.2)].

5.10 Immune Reconstitution Syndrome

Immune reconstitution syndrome has been reported in patients treated with combination antiretroviral therapy, including REYATAZ. During the initial phase of combination antiretroviral treatment, patients whose immune system responds may develop an inflammatory response to indolent or residual opportunistic infections (such as Mycobacterium avium, cytomegalovirus, Pneumocystis jirovecii pneumonia, or tuberculosis), which may necessitate further evaluation and treatment.

Autoimmune disorders (such as Graves’ disease, polymyositis, Guillain-Barré syndrome, and autoimmune hepatitis) have also been reported to occur in the setting of immune reconstitution; however, the time to onset is more variable, and can occur many months after initiation of treatment.

5.11 Fat Redistribution

Redistribution/accumulation of body fat including central obesity, dorsocervical fat enlargement (buffalo hump), peripheral wasting, facial wasting, breast enlargement, and “cushingoid appearance” have been observed in patients receiving antiretroviral therapy. The mechanism and long-term consequences of these events are currently unknown. A causal relationship has not been established.

5.12 Hemophilia

There have been reports of increased bleeding, including spontaneous skin hematomas and hemarthrosis, in patients with hemophilia type A and B treated with protease inhibitors. In some patients, additional factor VIII was given. In more than half of the reported cases, treatment with protease inhibitors was continued or reintroduced. A causal relationship between protease inhibitor therapy and these events has not been established.

5.13 Resistance/Cross-Resistance

Various degrees of cross-resistance among protease inhibitors have been observed. Resistance to atazanavir may not preclude the subsequent use of other protease inhibitors [see Microbiology (12.4)].

6 ADVERSE REACTIONS

The following adverse reactions are discussed in greater detail in other sections of the labeling:

- cardiac conduction abnormalities [see Warnings and Precautions (5.1)]
- rash [see Warnings and Precautions (5.2)]
- hyperbilirubinemia [see Warnings and Precautions (5.8)]
- chronic kidney disease [see Warnings and Precautions (5.5)]
- nephrolithiasis and cholelithiasis [see Warnings and Precautions (5.6)]

6.1 Clinical Trial Experience

Because clinical trials are conducted under widely varying conditions, adverse reaction rates observed in the clinical trials of a drug cannot be directly compared to rates in the clinical trials of another drug and may not reflect the rates observed in practice.

Adverse Reactions in Treatment-Naive Adult Participants

The safety profile of REYATAZ in treatment-naive adults is based on 1625 participants with HIV-1 in clinical trials. 536 participants received REYATAZ 300 mg with ritonavir 100 mg and 1089 participants received REYATAZ 400 mg or higher (without ritonavir).

The most common adverse reactions were nausea, jaundice/scleral icterus, and rash.

Selected clinical adverse reactions of moderate or severe intensity reported in ≥ 2% of treatment-naive participants receiving combination therapy including REYATAZ 300 mg with ritonavir 100 mg and REYATAZ 400 mg (without ritonavir) are presented in Tables 7 and 8, respectively.

Table 7: Selected Adverse Reactionsa of Moderate or Severe Intensity Reported in ≥2% of Adult Treatment-Naive Participants with HIV-1,b Study AI424-138
 | 96 weeksc REYATAZ 300 mg with ritonavir 100 mg (once daily) and tenofovir DF/emtricitabined (n=441) | 96 weeksc lopinavir/ritonavird 400 mg/100 mg (twice daily) and tenofovir DF/emtricitabinee (n=437)
Digestive System
Nausea | 4% | 8%
Jaundice/scleral icterus | 5% | *
Diarrhea | 2% | 12%
Skin and Appendages
Rash | 3% | 2%
* None reported in this treatment arm.
a Includes events of possible, probable, certain, or unknown relationship to treatment regimen.
b Based on the regimen containing REYATAZ.
c Median time on therapy.
d Administered as a fixed-dose.
e As a fixed-dose product: 300 mg tenofovir DF, 200 mg emtricitabine once daily.

Table 8: Selected Adverse Reactionsa of Moderate or Severe Intensity Reported in ≥2% of Adult Treatment-Naive Participants with HIV-1,b Studies AI424-034, AI424-007, and AI424-008
 | Study AI424-034 |  | Studies AI424-007, -008
 | 64 weeksc; REYATAZ 400 mg (once daily) with lamivudine/ zidovudinee (n=404) | 64 weeksc; efavirenz 600 mg (once daily) with lamivudine/ zidovudinee (n=401) | 120 weeksc,d; REYATAZ 400 mg (once daily) with stavudine and lamivudine or didanosine (n=279) | 73 weeksc,d; nelfinavir 750 mg TID or 1250 mg BID with stavudine and lamivudine or didanosine (n=191)
Body as a Whole
Headache | 6% | 6% | 1% | 2%
Digestive System
Nausea | 14% | 12% | 6% | 4%
Jaundice/scleral icterus | 7% | * | 7% | *
Vomiting | 4% | 7% | 3% | 3%
Abdominal pain | 4% | 4% | 4% | 2%
Diarrhea | 1% | 2% | 3% | 16%
Nervous System
Insomnia | 3% | 3% | <1% | *
Dizziness | 2% | 7% | <1% | *
Peripheral neurologic symptoms | <1% | 1% | 4% | 3%
Skin and Appendages
Rash | 7% | 10% | 5% | 1%
* None reported in this treatment arm.
a Includes events of possible, probable, certain, or unknown relationship to treatment regimen.
b Based on regimens containing REYATAZ.
c Median time on therapy.
d Includes long-term follow-up.
e As a fixed-dose product: 150 mg lamivudine/300 mg zidovudine twice daily.

Adverse Reactions in Treatment-Experienced Adult Participants

The safety profile of REYATAZ in treatment-experienced adults with HIV-1 is based on 119 participants with HIV-1 in clinical trials.

The most common adverse reactions are jaundice/scleral icterus and myalgia.

Selected clinical adverse reactions of moderate or severe intensity reported in ≥2% of treatment-experienced participants receiving REYATAZ with ritonavir are presented in Table 9.

Table 9: Selected Adverse Reactionsa of Moderate or Severe Intensity Reported in ≥2% of Adult Treatment-Experienced Participants with HIV-1,b Study AI424-045
 | 48 weeksc REYATAZ with ritonavir 300/100 mg (once daily) and tenofovir DF and NRTI (n=119) | 48 weeksc lopinavir/ritonavir 400/100 mg (twice dailyd) and tenofovir DF and NRTI (n=118)
Body as a Whole
Fever | 2% | *
Digestive System
Jaundice/scleral icterus | 9% | *
Diarrhea | 3% | 11%
Nausea | 3% | 2%
Nervous System
Depression | 2% | <1%
Musculoskeletal System
Myalgia | 4% | *
* None reported in this treatment arm.
a Includes events of possible, probable, certain, or unknown relationship to treatment regimen.
b Based on the regimen containing REYATAZ.
c Median time on therapy.
d As a fixed-dose product.

Laboratory Abnormalities in Treatment-Naive Participants

The percentages of adult treatment-naive participants with HIV-1 treated with combination therapy, including REYATAZ 300 mg with ritonavir 100 mg or REYATAZ 400 mg (without ritonavir) with Grade 3–4 laboratory abnormalities, are presented in Tables 10 and 11, respectively.

Table 10: Grade 3–4 Laboratory Abnormalities Reported in ≥2% of Adult Treatment-Naive Participants with HIV-1,a Study AI424-138
 |  | 96 weeksb; REYATAZ 300 mg with ritonavir 100 mg (once daily) and tenofovir DF/emtricitabinec | 96 weeksb; lopinavir/ritonavir 400 mg/100 mgc (twice daily) and tenofovir DF/emtricitabined
Variable | Limite | (n=441) | (n=437)
Chemistry | High
SGOT/AST | ≥5.1 × ULN | 3% | 1%
SGPT/ALT | ≥5.1 × ULN | 3% | 2%
Total Bilirubin | ≥2.6 × ULN | 44% | <1%
Lipase | ≥2.1 × ULN | 2% | 2%
Creatine Kinase | ≥5.1 × ULN | 8% | 7%
Total Cholesterol | ≥240 mg/dL | 11% | 25%
Hematology | Low
Neutrophils | <750 cells/mm^3 | 5% | 2%
a Based on the regimen containing REYATAZ.
b Median time on therapy.
c Administered as a fixed-dose product.
d As a fixed-dose product: 300 mg tenofovir DF, 200 mg emtricitabine once daily.
e ULN=upper limit of normal.

Table 11: Grade 3–4 Laboratory Abnormalities Reported in ≥2% of Adult Treatment-Naive Participants with HIV-1,a Studies AI424-034, AI424-007, and AI424-008
 |  | Study AI424-034 |  | Studies AI424-007, -008
 |  | 64 weeksb; REYATAZ 400 mg; once daily and lamivudine/zidovudinee | 64 weeksb; efavirenz 600 mg once daily and lamivudine/zidovudinee | 120 weeksb,c; REYATAZ 400 mg once daily with stavudine and lamivudine or with stavudine and didanosine | 73 weeksb,c; nelfinavir 750 mg TID or 1250 mg BID with stavudine and lamivudine or with stavudine and didanosine
Variable | Limitd | (n=404) | (n=401) | (n=279) | (n=191)
Chemistry | High
SGOT/AST | ≥5.1 × ULN | 2% | 2% | 7% | 5%
SGPT/ALT | ≥5.1 × ULN | 4% | 3% | 9% | 7%
Total Bilirubin | ≥2.6 × ULN | 35% | <1% | 47% | 3%
Amylase | ≥2.1 × ULN | * | * | 14% | 10%
Lipase | ≥2.1 × ULN | <1% | 1% | 4% | 5%
Creatine Kinase | ≥5.1 × ULN | 6% | 6% | 11% | 9%
Total Cholesterol | ≥240 mg/dL | 6% | 24% | 19% | 48%
Triglycerides | ≥751 mg/dL | <1% | 3% | 4% | 2%
Hematology | Low
Hemoglobin | <8.0 g/dL | 5% | 3% | <1% | 4%
Neutrophils | <750 cells/mm^3 | 7% | 9% | 3% | 7%
* None reported in this treatment arm.
a Based on regimen(s) containing REYATAZ.
b Median time on therapy.
c Includes long-term follow-up.
d ULN = upper limit of normal.
e As a fixed-dose product: 150 mg lamivudine, 300 mg zidovudine twice daily.

Change in Lipids from Baseline in Treatment-Naive Participants with HIV-1

For Study AI424-138 and Study AI424-034, changes from baseline in LDL-cholesterol, HDL-cholesterol, total cholesterol, and triglycerides are shown in Tables 12 and 13, respectively.

Table 12: Lipid Values, Mean Change from Baseline, Study AI424-138
 | REYATAZ with ritonavira,b |  |  |  |  | lopinavir/ritonavirb,c
 | Baseline | Week 48 |  | Week 96 |  | Baseline | Week 48 |  | Week 96
 | mg/dL | mg/dL | Changed | mg/dL | Changed | mg/dL | mg/dL | Changed | mg/dL | Changed
 | (n=428e) | (n=372e) | (n=372e) | (n=342e) | (n=342e) | (n=424e) | (n=335e) | (n=335e) | (n=291e) | (n=291e)
LDL-Cholesterolf | 92 | 105 | +14% | 105 | +14% | 93 | 111 | +19% | 110 | +17%
HDL-Cholesterolf | 37 | 46 | +29% | 44 | +21% | 36 | 48 | +37% | 46 | +29%
Total Cholesterolf | 149 | 169 | +13% | 169 | +13% | 150 | 187 | +25% | 186 | +25%
Triglyceridesf | 126 | 145 | +15% | 140 | +13% | 129 | 194 | +52% | 184 | +50%
a REYATAZ 300 mg with ritonavir 100 mg once daily with the fixed-dose product: 300 mg tenofovir DF/ 200 mg emtricitabine once daily.
b Values obtained after initiation of serum lipid-reducing agents were not included in these analyses. At baseline, serum lipid-reducing agents were used in 1% in the lopinavir/ritonavir treatment arm and 1% in the REYATAZ with ritonavir arm. Through Week 48, serum lipid-reducing agents were used in 8% in the lopinavir/ritonavir treatment arm and 2% in the REYATAZ with ritonavir arm. Through Week 96, serum lipid-reducing agents were used in 10% in the lopinavir/ritonavir treatment arm and 3% in the REYATAZ with ritonavir arm.
c Lopinavir/ritonavir (400 mg/100 mg) twice daily with the fixed-dose product 300 mg tenofovir DF/200 mg emtricitabine once daily.
d The change from baseline is the mean of within-participant changes from baseline for participants with both baseline and Week 48 or Week 96 values and is not a simple difference of the baseline and Week 48 or Week 96 mean values, respectively.
e Number of participants with LDL-cholesterol measured.
f Fasting.

Table 13: Lipid Values, Mean Change from Baseline, Study AI424-034
 | REYATAZa,b |  |  | efavirenzb,c
 | Baseline mg/dL (n=383e) | Week 48 mg/dL (n=283e) | Week 48 Changed (n=272e) | Baseline mg/dL (n=378e) | Week 48 mg/dL (n=264e) | Week 48 Changed (n=253e)
LDL-Cholesterolf | 98 | 98 | +1% | 98 | 114 | +18%
HDL-Cholesterol | 39 | 43 | +13% | 38 | 46 | +24%
Total Cholesterol | 164 | 168 | +2% | 162 | 195 | +21%
Triglyceridesf | 138 | 124 | −9% | 129 | 168 | +23%
a REYATAZ 400 mg once daily with the fixed-dose product: 150 mg lamivudine, 300 mg zidovudine twice daily.
b Values obtained after initiation of serum lipid-reducing agents were not included in these analyses. At baseline, serum lipid-reducing agents were used in 0% in the efavirenz treatment arm and <1% in the REYATAZ arm. Through Week 48, serum lipid-reducing agents were used in 3% in the efavirenz treatment arm and 1% in the REYATAZ arm.
c Efavirenz 600 mg once daily with the fixed-dose product: 150 mg lamivudine/300 mg zidovudine twice daily.
d The change from baseline is the mean of within-participant changes from baseline for participants with both baseline and Week 48 values and is not a simple difference of the baseline and Week 48 mean values.
e Number of participants with LDL-cholesterol measured.
f Fasting.

Laboratory Abnormalities in Treatment-Experienced Participants with HIV-1

The percentages of adult treatment-experienced participants with HIV-1 treated with combination therapy, including REYATAZ with ritonavir having Grade 3–4 laboratory abnormalities, are presented in Table 14.

Table 14: Grade 3–4 Laboratory Abnormalities Reported in ≥2% of Adult Treatment-Experienced Participants with HIV-1, Study AI424-045a
 |  | 48 weeksb | 48 weeksb
 |  | REYATAZ with ritonavir 300/100 mg (once daily) and tenofovir DF and NRTI | lopinavir/ritonavir 400/100 mg (twice dailyd) and tenofovir DF and NRTI
Variable | Limitc | (n=119) | (n=118)
Chemistry | High
SGOT/AST | ≥5.1 × ULN | 3% | 3%
SGPT/ALT | ≥5.1 × ULN | 4% | 3%
Total Bilirubin | ≥2.6 × ULN | 49% | <1%
Lipase | ≥2.1 × ULN | 5% | 6%
Creatine Kinase | ≥5.1 × ULN | 8% | 8%
Total Cholesterol | ≥240 mg/dL | 25% | 26%
Triglycerides | ≥751 mg/dL | 8% | 12%
Glucose | ≥251 mg/dL | 5% | <1%
Hematology | Low
Platelets | <50,000 cells/mm^3 | 2% | 3%
Neutrophils | <750 cells/mm^3 | 7% | 8%
a Based on regimen(s) containing REYATAZ.
b Median time on therapy.
c ULN = upper limit of normal.
d As a fixed-dose product.

Change in Lipids from Baseline in Treatment-Experienced Participants with HIV-1

For Study AI424-045, changes from baseline in LDL-cholesterol, HDL-cholesterol, total cholesterol, and triglycerides are shown in Table 15. The observed magnitude of dyslipidemia was less with REYATAZ with ritonavir than with lopinavir/ritonavir. However, the clinical impact of such findings has not been demonstrated.

Table 15: Lipid Values, Mean Change from Baseline, Study AI424-045
 | REYATAZ with ritonavira,b |  |  | Lopinavir/ritonavirb,c
 | Baseline mg/dL (n=111e) | Week 48 mg/dL (n=75e) | Week 48 Changed (n=74e) | Baseline mg/dL (n=108e) | Week 48 mg/dL (n=76e) | Week 48 Changed (n=73e)
LDL-Cholesterolf | 108 | 98 | −10% | 104 | 103 | +1%
HDL-Cholesterol | 40 | 39 | −7% | 39 | 41 | +2%
Total Cholesterol | 188 | 170 | −8% | 181 | 187 | +6%
Triglyceridesf | 215 | 161 | −4% | 196 | 224 | +30%
a REYATAZ 300 mg once daily with ritonavir and tenofovir DF, and 1 NRTI.
b Values obtained after initiation of serum lipid-reducing agents were not included in these analyses. At baseline, serum lipid-reducing agents were used in 4% in the lopinavir/ritonavir treatment arm and 4% in the REYATAZ with ritonavir arm. Through Week 48, serum lipid-reducing agents were used in 19% in the lopinavir/ritonavir treatment arm and 8% in the REYATAZ with ritonavir arm.
c Lopinavir/ritonavir (400/100 mg), as a fixed dose regimen, BID with tenofovir DF and 1 NRTI.
d The change from baseline is the mean of within-participant changes from baseline for participants with both baseline and Week 48 values and is not a simple difference of the baseline and Week 48 mean values.
e Number of participants with LDL-cholesterol measured.
f Fasting.

Adverse Reactions in Pediatric Participants with HIV-1: REYATAZ Capsules

The safety and tolerability of REYATAZ Capsules with and without ritonavir have been established in pediatric participants with HIV-1, at least 6 years of age from the open-label, multicenter clinical trial PACTG 1020A.

The safety profile of REYATAZ in pediatric participants with HIV-1 (6 to less than 18 years of age) taking the capsule formulation was generally similar to that observed in clinical studies of REYATAZ in adults. The most common Grade 2–4 adverse events (≥5%, regardless of causality) reported in pediatric participants were cough (21%), fever (18%), jaundice/scleral icterus (15%), rash (14%), vomiting (12%), diarrhea (9%), headache (8%), peripheral edema (7%), extremity pain (6%), nasal congestion (6%), oropharyngeal pain (6%), wheezing (6%), and rhinorrhea (6%). Asymptomatic second-degree atrioventricular block was reported in <2% of participants. The most common Grade 3–4 laboratory abnormalities occurring in pediatric participants taking the capsule formulation were elevation of total bilirubin (≥3.2 mg/dL, 58%), neutropenia (9%), and hypoglycemia (4%). All other Grade 3–4 laboratory abnormalities occurred with a frequency of less than 3%.

Adverse Reactions in Pediatric Participants with HIV-1: REYATAZ Oral Powder

The data described below reflect exposure to REYATAZ oral powder in 155 participants weighing at least 5 kg to less than 35 kg, including 134 participants exposed for 48 weeks. These data are from two pooled, open-label, multi-center clinical trials in treatment-naive and treatment-experienced pediatric participants with HIV-1 (AI424-397 [PRINCE I] and AI424-451 [PRINCE II]). Age ranged from 3 months to 10 years of age. In these studies, 51% were female and 49% were male. All participants received ritonavir and 2 nucleoside reverse transcriptase inhibitors (NRTIs).

The safety profile of REYATAZ in pediatric participants taking REYATAZ oral powder was generally similar to that observed in clinical studies of REYATAZ in pediatric participants taking REYATAZ capsules. The most common Grade 3–4 laboratory abnormalities occurring in pediatric participants weighing 5 kg to less than 35 kg taking REYATAZ oral powder were increased amylase (33%), neutropenia (9%), increased SGPT/ALT (9%), elevation of total bilirubin (≥2.6 times ULN, 16%), and increased lipase (8%). All other Grade 3–4 laboratory abnormalities occurred with a frequency of less than 3%.

Adverse Reactions in Participants with HIV-1 and Hepatitis B and/or Hepatitis C Virus

In Study AI424-138, 60 participants administered REYATAZ 300 mg with ritonavir 100 mg once daily, and 51 participants treated with lopinavir/ritonavir 400 mg/100 mg (as fixed-dose product) twice daily, each with fixed-dose tenofovir DF/emtricitabine, were seropositive for hepatitis B and/or C at study entry. ALT levels >5 times ULN developed in 10% (6/60) of the participants administered REYATAZ with ritonavir and 8% (4/50) of the participants treated with lopinavir/ritonavir. AST levels >5 times ULN developed in 10% (6/60) of the participants administered REYATAZ with ritonavir and none (0/50) of the participants treated with lopinavir/ritonavir.

In Study AI424-045, 20 participants administered REYATAZ 300 mg with ritonavir 100 mg once daily, and 18 participants treated with lopinavir/ritonavir 400 mg/100 mg twice daily (as fixed-dose product), were seropositive for hepatitis B and/or C at study entry. ALT levels >5 times ULN developed in 25% (5/20) of the participants administered REYATAZ with ritonavir and 6% (1/18) of the participants treated with lopinavir/ritonavir treated. AST levels >5 times ULN developed in 10% (2/20) of the participants administered REYATAZ with ritonavir and 6% (1/18) of the participants treated with lopinavir/ritonavir.

In Studies AI424-008 and AI424-034, 74 participants treated with REYATAZ 400 mg once daily, 58 who received efavirenz, and 12 who received nelfinavir were seropositive for hepatitis B and/or C at study entry. ALT levels >5 times ULN developed in 15% of the participants treated with REYATAZ, 14% of the participants treated with efavirenz, and 17% of the participants treated with nelfinavir. AST levels >5 times ULN developed in 9% of the participants treated with REYATAZ, 5% of the participants treated with efavirenz, and 17% of the participants treated with nelfinavir. Within REYATAZ and control regimens, no difference in frequency of bilirubin elevations was noted between seropositive and seronegative participants [see Warnings and Precautions (5.8)].

6.2 Postmarketing Experience

The following events have been identified during postmarketing use of REYATAZ. Because these reactions are reported voluntarily from a population of unknown size, it is not always possible to reliably estimate their frequency or establish a causal relationship to drug exposure.

Body as a Whole: edema

Cardiovascular System: second-degree AV block, third-degree AV block, left bundle branch block, QTc prolongation [see Warnings and Precautions (5.1)]

Gastrointestinal System: pancreatitis

Hepatic System: hepatic function abnormalities

Hepatobiliary Disorders: cholelithiasis [see Warnings and Precautions (5.6)], cholecystitis, cholestasis

Metabolic System and Nutrition Disorders: diabetes mellitus, hyperglycemia [see Warnings and Precautions (5.9)]

Musculoskeletal System: arthralgia

Renal System: nephrolithiasis [see Warnings and Precautions (5.6)], interstitial nephritis, granulomatous interstitial nephritis, chronic kidney disease [see Warnings and Precautions (5.5)]

Skin and Appendages: alopecia, maculopapular rash [see Contraindications (4) and Warnings and Precautions (5.2)], pruritus, angioedema

7 DRUG INTERACTIONS

7.1 Potential for REYATAZ to Affect Other Drugs

Atazanavir is an inhibitor of CYP3A and UGT1A1. Coadministration of REYATAZ and drugs primarily metabolized by CYP3A or UGT1A1 may result in increased plasma concentrations of the other drug that could increase or prolong its therapeutic and adverse effects.

Atazanavir is a weak inhibitor of CYP2C8. Use of REYATAZ without ritonavir is not recommended when coadministered with drugs highly dependent on CYP2C8 with narrow therapeutic indices (eg, paclitaxel, repaglinide). When REYATAZ with ritonavir is coadministered with substrates of CYP2C8, clinically significant interactions are not expected [see Clinical Pharmacology, Table 22 (12.3)].

The magnitude of CYP3A-mediated drug interactions on coadministered drug may change when REYATAZ is coadministered with ritonavir. See the complete prescribing information for ritonavir for information on drug interactions with ritonavir.

7.2 Potential for Other Drugs to Affect REYATAZ

Atazanavir is a CYP3A4 substrate; therefore, drugs that induce CYP3A4 may decrease atazanavir plasma concentrations and reduce REYATAZ’s therapeutic effect (see Table 16).

Atazanavir solubility decreases as pH increases. Reduced plasma concentrations of atazanavir are expected if proton-pump inhibitors, antacids, buffered medications, or H2-receptor antagonists are administered with REYATAZ [see Dosage and Administration (2.3, 2.4, 2.5 and 2.6)].

7.3 Established and Other Potentially Significant Drug Interactions

Table 16 provides dosing recommendations in adults as a result of drug interactions with REYATAZ. These recommendations are based on either drug interaction studies or predicted interactions due to the expected magnitude of interaction and potential for serious events or loss of efficacy.

Table 16: Established and Other Potentially Significant Drug Interactions: Alteration in Dose or Regimen May Be Recommended Based on Drug Interaction Studiesa or Predicted Interactions (Information in the table applies to REYATAZ with or without ritonavir, unless otherwise indicated)
Concomitant Drug Class: Specific Drugs | Effect on Concentration of Atazanavir or Concomitant Drug | Clinical Comment
HIV Antiviral Agents
Nucleoside Reverse Transcriptase Inhibitors (NRTIs): didanosine buffered formulations enteric coated (EC) capsules | ↓ atazanavir ↓ didanosine | It is recommended that REYATAZ be given (with food) 2 h before or 1 h after didanosine buffered formulations. Simultaneous administration of didanosine EC and REYATAZ with food results in a decrease in didanosine exposure. Thus, REYATAZ and didanosine EC should be administered at different times.
Nucleotide Reverse Transcriptase Inhibitors: tenofovir disoproxil fumarate (DF) | ↓ atazanavir ↑ tenofovir | When coadministered with tenofovir DF in adults, it is recommended that REYATAZ 300 mg be given with ritonavir 100 mg and tenofovir DF 300 mg (all as a single daily dose with food). The mechanism of this interaction is unknown. Higher tenofovir concentrations could potentiate tenofovir-associated adverse reactions, including renal disorders. Patients receiving REYATAZ and tenofovir DF should be monitored for tenofovir-associated adverse reactions. For pregnant patients taking REYATAZ with ritonavir and tenofovir DF, see Dosage and Administration (2.6).
Non-nucleoside Reverse Transcriptase Inhibitors (NNRTIs): efavirenz | ↓ atazanavir | In HIV-treatment-naive adult patients:; If REYATAZ is combined with efavirenz, REYATAZ 400 mg (two 200-mg capsules) should be administered with ritonavir 100 mg simultaneously once daily with food, and efavirenz 600 mg should be administered once daily on an empty stomach, preferably at bedtime.; In HIV-treatment-experienced adult patients:; Coadministration of REYATAZ with efavirenz is not recommended.
nevirapine | ↓ atazanavir; ↑ nevirapine | Coadministration of REYATAZ with nevirapine is contraindicated due to the potential loss of virologic response and development of resistance, as well as the potential risk for nevirapine-associated adverse reactions [see Contraindications (4)].
Protease Inhibitors: saquinavir (soft gelatin capsules) | ↑ saquinavir | Appropriate dosing recommendations for this combination, with or without ritonavir, with respect to efficacy and safety have not been established. In a clinical study, saquinavir 1200 mg coadministered with REYATAZ 400 mg and tenofovir DF 300 mg (all given once daily), and nucleoside analogue reverse transcriptase inhibitors did not provide adequate efficacy [see Clinical Studies (14.2)].
indinavir |  | Coadministration of REYATAZ with indinavir is contraindicated. Both REYATAZ and indinavir are associated with indirect (unconjugated) hyperbilirubinemia [see Contraindications (4)].
ritonavir | ↑ atazanavir | If REYATAZ is coadministered with ritonavir, it is recommended that REYATAZ 300 mg once daily be given with ritonavir 100 mg once daily with food in adults. See the complete prescribing information for ritonavir for information on drug interactions with ritonavir.
Others | ↑ other protease inhibitor | Coadministration with other protease inhibitors is not recommended.
Hepatitis C Antiviral Agents
elbasvir/grazoprevir | ↑ grazoprevir | Coadministration of REYATAZ with grazoprevir is contraindicated due to the potential for increased risk of ALT elevations [see Contraindications (4)].
glecaprevir/pibrentasvir | ↑ glecaprevir; ↑ pibrentasvir | Coadministration of REYATAZ with glecaprevir/pibrentasvir is contraindicated due to the potential for increased the risk of ALT elevations [see Contraindications (4)].
voxilaprevir/sofosbuvir/velpatasvir | ↑ voxilaprevir | Coadministration with REYATAZ is not recommended.
Other Agents
Alpha 1-Adrenoreceptor Antagonist: alfuzosin | ↑ alfuzosin | Coadministration of REYATAZ with alfuzosin is contraindicated due to risk for hypotension [see Contraindications (4)].
Antacids and buffered medications: | ↓ atazanavir | REYATAZ should be administered 2 hours before or 1 hour after antacids and buffered medications.
Antiarrhythmics: amiodarone, quinidine; amiodarone, bepridil, lidocaine (systemic), quinidine | ↑ amiodarone, bepridil, lidocaine (systemic), quinidine | Concomitant use of REYATAZ with ritonavir and either quinidine or amiodarone is contraindicated due to the potential for serious or life-threatening reactions such as cardiac arrhythmias [see Contraindications (4)].; Coadministration with REYATAZ without ritonavir has the potential to produce serious and/or life-threatening adverse events but has not been studied. Caution is warranted and therapeutic concentration monitoring of these drugs is recommended if they are used concomitantly with REYATAZ without ritonavir.
Anticoagulants: warfarin | ↑ warfarin | Coadministration with REYATAZ has the potential to produce serious and/or life-threatening bleeding and has not been studied. It is recommended that International Normalized Ratio (INR) be monitored.
Direct-Acting Oral Anticoagulants: betrixaban, dabigatran, edoxaban | ↑ betrixaban; ↑ dabigatran; ↑ edoxaban | Concomitant use of REYATAZ with ritonavir, a strong CYP3A4/P-gp inhibitor, may result in an increased risk of bleeding. Refer to the respective DOAC prescribing information regarding dosing instructions for coadministration with P-gp inhibitors.
rivaroxaban | REYATAZ with ritonavir; ↑ rivaroxaban | Coadministration of REYATAZ with ritonavir, a strong CYP3A4/P-gp inhibitor, and rivaroxaban is not recommended, as it may result in an increased risk of bleeding.
 | REYATAZ; ↑ rivaroxaban | Coadministration of REYATAZ, a CYP3A4 inhibitor, and rivaroxaban may result in an increased risk of bleeding. Close monitoring is recommended when REYATAZ is coadministered with rivaroxaban.
apixaban | REYATAZ with ritonavir; ↑ apixaban | Concomitant use of REYATAZ with ritonavir, a strong CYP3A4/P-gp inhibitor, may result in an increased risk of bleeding. Refer to apixaban dosing instructions for coadministration with strong CYP3A4 and P-gp inhibitors in the apixaban prescribing information.
 | REYATAZ; ↑ apixaban | Concomitant use of REYATAZ, a CYP3A4 inhibitor, and apixaban may result in an increased risk of bleeding. Close monitoring is recommended when apixaban is coadministered with REYATAZ.
Antidepressants: tricyclic antidepressants | ↑ tricyclic antidepressants | Coadministration with REYATAZ has the potential to produce serious and/or life-threatening adverse events and has not been studied. Concentration monitoring of these drugs is recommended if they are used concomitantly with REYATAZ.
trazodone | ↑ trazodone | Nausea, dizziness, hypotension, and syncope have been observed following coadministration of trazodone with ritonavir. If trazodone is used with a CYP3A4 inhibitor such as REYATAZ, the combination should be used with caution and a lower dose of trazodone should be considered.
Antiepileptics: carbamazepine | ↓ atazanavir ↑ carbamazepine | Coadministration of REYATAZ (with or without ritonavir) with carbamazepine is contraindicated due to the risk for loss of virologic response and development of resistance [see Contraindications (4)].
phenytoin, phenobarbital | ↓ atazanavir ↓ phenytoin ↓ phenobarbital | Coadministration of REYATAZ (with or without ritonavir) with phenytoin or phenobarbital is contraindicated due to the risk for loss of virologic response and development of resistance [see Contraindications (4)].
lamotrigine | ↓ lamotrigine | Coadministration of lamotrigine and REYATAZ with ritonavir may require dosage adjustment of lamotrigine. No dose adjustment of lamotrigine is required when coadministered with REYATAZ without ritonavir.
Antifungals: ketoconazole, itraconazole | REYATAZ with ritonavir: ↑ ketoconazole ↑ itraconazole | Coadministration of ketoconazole has only been studied with REYATAZ without ritonavir (negligible increase in atazanavir AUC and Cmax). Due to the effect of ritonavir on ketoconazole, high doses of ketoconazole and itraconazole (>200 mg/day) should be used cautiously when administering REYATAZ with ritonavir.
voriconazole | REYATAZ with ritonavir in participants with a functional CYP2C19 allele: ↓ voriconazole ↓ atazanavir REYATAZ with ritonavir in participants without a functional CYP2C19 allele: ↑ voriconazole ↓ atazanavir | The use of voriconazole in patients receiving REYATAZ with ritonavir is not recommended unless an assessment of the benefit/risk to the patient justifies the use of voriconazole. Patients should be carefully monitored for voriconazole-associated adverse reactions and loss of either voriconazole or atazanavir efficacy during the coadministration of voriconazole and REYATAZ with ritonavir. Coadministration of voriconazole with REYATAZ (without ritonavir) may affect atazanavir concentrations; however, no data are available.
Antigout: colchicine | ↑ colchicine | The coadministration of REYATAZ with colchicine in patients with renal or hepatic impairment is not recommended.; Recommended adult dosage of colchicine when administered with REYATAZ:; Treatment of gout flares:; 0.6 mg (1 tablet) for 1 dose, followed by 0.3 mg (half tablet) 1 hour later. Not to be repeated before 3 days.; Prophylaxis of gout flares:; If the original regimen was 0.6 mg twice a day, the regimen should be adjusted to 0.3 mg once a day.; If the original regimen was 0.6 mg once a day, the regimen should be adjusted to 0.3 mg once every other day.; Treatment of familial Mediterranean fever (FMF):; Maximum daily dose of 0.6 mg (may be given as 0.3 mg twice a day).
Antimycobacterials: rifampin | ↓ atazanavir | Coadministration of REYATAZ with rifampin is contraindicated due to the risk for loss of virologic response and development of resistance [see Contraindications (4)].
rifabutin | ↑ rifabutin | A rifabutin dose reduction of up to 75% (eg, 150 mg every other day or 3 times per week) is recommended. Increased monitoring for rifabutin-associated adverse reactions including neutropenia is warranted.
Antineoplastics:; irinotecan | ↑ irinotecan | Coadministration of REYATAZ with irinotecan is contraindicated. Atazanavir inhibits UGT1A1 and may interfere with the metabolism of irinotecan, resulting in increased irinotecan toxicities [see Contraindications (4)].
apalutamide | ↓ atazanavir | Coadministration of REYATAZ (with or without ritonavir) and apalutamide is contraindicated due to the potential for subsequent loss of virologic response and possible resistance to the class of protease inhibitors [see Contraindications (4)].
ivosidenib | ↓ atazanavir; ↑ ivosidenib | Coadministration of ivosidenib with REYATAZ (with or without ritonavir) is contraindicated due to the potential for loss of virologic response and risk of serious adverse events such as QT interval prolongation.
encorafenib | ↓ atazanavir; ↑ encorafenib | Coadministration of encorafenib with REYATAZ (with or without ritonavir) is contraindicated due to the potential for the loss of virologic response and risk of serious adverse events such as QT interval prolongation.
Antiplatelets:
ticagrelor | ↑ ticagrelor | Coadministration with ticagrelor is not recommended due to potential increase in the risk of dyspnea, bleeding and other adverse events associated with ticagrelor.
clopidogrel | ↓ clopidogrel active metabolite | Coadministration of REYATAZ (with or without ritonavir) and clopidogrel is not recommended. This is due to the potential reduction of the antiplatelet activity of clopidogrel.
Antipsychotics:; pimozide | ↑ pimozide | Coadministration of REYATAZ with pimozide is contraindicated. This is due to the potential for serious and/or life-threatening reactions such as cardiac arrhythmias [see Contraindications (4)].
lurasidone | REYATAZ with ritonavir; ↑ lurasidone | REYATAZ with ritonavir Coadministration of lurasidone with REYATAZ with ritonavir is contraindicated. This is due to the potential for serious and/or life-threatening reactions [see Contraindications (4)].
 | REYATAZ; ↑ lurasidone | REYATAZ without ritonavir; If coadministration is necessary, reduce the lurasidone dose. Refer to the lurasidone prescribing information for concomitant use with moderate CYP3A4 inhibitors.
quetiapine | ↑ quetiapine | Initiation of REYATAZ with ritonavir in patients taking quetiapine:; Consider alternative antiretroviral therapy to avoid increases in quetiapine exposures. If coadministration is necessary, reduce the quetiapine dose to 1/6 of the current dose and monitor for quetiapine-associated adverse reactions. Refer to the quetiapine prescribing information for recommendations on adverse reaction monitoring.; Initiation of quetiapine in patients taking REYATAZ with ritonavir:; Refer to the quetiapine prescribing information for initial dosing and titration of quetiapine.
Benzodiazepines:; midazolam (oral); triazolam | ↑ midazolam; ↑ triazolam | Coadministration of REYATAZ with either orally administered midazolam or triazolam is contraindicated. Triazolam and orally administered midazolam are extensively metabolized by CYP3A4, and coadministration with REYATAZ can lead to the potential for serious and/or life-threatening events such as prolonged or increased sedation or respiratory depression [see Contraindications (4)].
parenterally administered midazolamb | ↑ midazolam | Coadministration with parenteral midazolam should be done in a setting which ensures close clinical monitoring and appropriate medical management in case of respiratory depression and/or prolonged sedation. Dosage reduction for midazolam should be considered, especially if more than a single dose of midazolam is administered.
Calcium channel blockers: diltiazem | ↑ diltiazem and desacetyl-diltiazem | Caution is warranted. A dose reduction of diltiazem by 50% should be considered. ECG monitoring is recommended. Coadministration of diltiazem and REYATAZ with ritonavir has not been studied.
felodipine, nifedipine, nicardipine, and verapamil | ↑ calcium channel blocker | Caution is warranted. Dose titration of the calcium channel blocker should be considered. ECG monitoring is recommended.
Corticosteroids:; dexamethasone and other corticosteroids (all routes of administration) | ↓ atazanavir; ↑ corticosteroids | Coadministration with dexamethasone or other corticosteroids that induce CYP3A may result in loss of therapeutic effect of REYATAZ and development of resistance to atazanavir and/or ritonavir. Alternative corticosteroids should be considered. Coadministration with corticosteroids (all routes of administration) that are metabolized by CYP3A, particularly for long-term use, may increase the risk for development of systemic corticosteroid effects including Cushing’s syndrome and adrenal suppression. Consider the potential benefit of treatment versus the risk of systemic corticosteroid effects. For coadministration of cutaneously administered corticosteroids sensitive to CYP3A inhibition, refer to the prescribing information of the corticosteroid for additional information.
Endothelin receptor antagonists: bosentan | REYATAZ; ↓ atazanavir; REYATAZ with ritonavir ↑ bosentan | Coadministration of bosentan and REYATAZ without ritonavir is not recommended.; For adult patients who have been receiving REYATAZ with ritonavir for at least 10 days, start bosentan at 62.5 mg once daily or every other day based on individual tolerability. For adult patients who have been receiving bosentan, discontinue bosentan at least 36 hours before starting REYATAZ with ritonavir. At least 10 days after starting REYATAZ with ritonavir, resume bosentan at 62.5 mg once daily or every other day based on individual tolerability.
Ergot derivatives:; dihydroergotamine, ergotamine, ergonovine, methylergonovine | ↑ ergot derivatives | Coadministration of REYATAZ with ergot derivatives is contraindicated. This is due to the potential for serious and/or life-threatening events such as acute ergot toxicity characterized by peripheral vasospasm and ischemia of the extremities and other tissues [see Contraindications (4)].
GI Motility Agents:; cisapride | ↑ cisapride | Coadministration of REYATAZ with cisapride is contraindicated. This is due to the potential for serious and/or life-threatening reactions such as cardiac arrhythmias [see Contraindications (4)].
Gonadotropin-releasing hormone Receptor (GnRH) Antagonists:; elagolix | ↓ atazanavir; ↑ elagolix | Coadministration of elagolix and REYATAZ with or without ritonavir is not recommended due to the potential of loss of virologic response and the potential risk of adverse events such as bone loss and hepatic transaminase elevations associated with elagolix.; In the event coadministration is necessary, limit concomitant use of elagolix 200mg twice daily with REYATAZ with or without ritonavir for up to 1 month or limit concomitant use of elagolix 150 mg once daily with REYATAZ (with or without ritonavir) for up to 6 months and monitor virologic response.
Herbal Products:; St. John’s wort (Hypericum perforatum) | ↓ atazanavir | Coadministration of products containing St. John’s wort with REYATAZ is contraindicated. This may result in loss of therapeutic effect of REYATAZ and the development of resistance [see Contraindications (4)].
Kinase inhibitors:; fostamatinib | ↑ R406 (active metabolite of fostamatinib) | When coadministering fostamatinib with REYATAZ (with or without ritonavir), monitor for toxicities of R406 exposure resulting in dose-related adverse events such as hepatotoxicity and neutropenia. Fostamatinib dose reduction may be required.
Lipid-modifying agents; HMG-CoA reductase inhibitors: lovastatin, simvastatin | ↑ lovastatin; ↑ simvastatin | Coadministration of REYATAZ with lovastatin or simvastatin is contraindicated. This is due to the potential for serious reactions such as myopathy, including rhabdomyolysis [see Contraindications (4)].
atorvastatin, rosuvastatin | ↑ atorvastatin ↑ rosuvastatin | Titrate atorvastatin dose carefully and use the lowest necessary dose. Rosuvastatin dose should not exceed 10 mg/day. The risk of myopathy, including rhabdomyolysis, may be increased when HIV protease inhibitors, including REYATAZ, are used in combination with these drugs.
Other Lipid Modifying Agents: lomitapide | ↑ lomitapide | Coadministration of REYATAZ with lomitapide is contraindicated. This is due to the potential for risk of markedly increased transaminase levels and hepatotoxicity associated with increased plasma concentrations of lomitapide. The mechanism of interaction is CYP3A4 inhibition by atazanavir and/or ritonavir [see Contraindications (4)].
H2-Receptor antagonists | ↓ atazanavir | Coadministration may result in loss of virologic response and development of resistance.; In HIV-treatment-naive adult patients:; REYATAZ 300 mg with ritonavir 100 mg once daily with food should be administered simultaneously with, and/or at least 10 hours after, a dose of the H2-receptor antagonist (H2RA). An H2RA dose comparable to famotidine 20 mg once daily up to a dose comparable to famotidine 40 mg twice daily can be used with REYATAZ 300 mg with ritonavir 100 mg in treatment-naive patients.; OR; For patients unable to tolerate ritonavir, REYATAZ 400 mg once daily with food should be administered at least 2 hours before and at least 10 hours after a dose of the H2RA. No single dose of the H2RA should exceed a dose comparable to famotidine 20 mg, and the total daily dose should not exceed a dose comparable to famotidine 40 mg. The use of REYATAZ without ritonavir in pregnant patients is not recommended.; In treatment-experienced adult patients:; Whenever an H2RA is given to a patient receiving REYATAZ with ritonavir, the H2RA dose should not exceed a dose comparable to famotidine 20 mg twice daily, and the REYATAZ with ritonavir doses should be administered simultaneously with, and/or at least 10 hours after, the dose of the H2RA.; - REYATAZ 300 mg with ritonavir 100 mg once daily (all as a single dose with food) if taken with an H2RA. - REYATAZ 400 mg with ritonavir 100 mg once daily (all as a single dose with food) if taken with both tenofovir DF and an H2RA. - REYATAZ 400 mg with ritonavir 100 mg once daily (all as a single dose with food) if taken with either tenofovir DF or an H2RA for pregnant patients during the second and third trimester. REYATAZ is not recommended for pregnant patients during the second and third trimester taking REYATAZ with both tenofovir DF and an H2RA.
Hormonal contraceptives: ethinyl estradiol and norgestimate or norethindrone | ↓ ethinyl estradiol ↑ norgestimatec; ↑ ethinyl estradiol ↑ norethindroned | Use caution if considering coadministration of oral contraceptives with REYATAZ or REYATAZ with ritonavir.; If REYATAZ with ritonavir is coadministered with an oral contraceptive, it is recommended that the oral contraceptive contain at least 35 mcg of ethinyl estradiol.; If REYATAZ is administered without ritonavir, the oral contraceptive should contain no more than 30 mcg of ethinyl estradiol.; Potential safety risks include substantial increases in progesterone exposure. The long-term effects of increases in concentration of the progestational agent are unknown and could increase the risk of insulin resistance, dyslipidemia, and acne.; Coadministration of REYATAZ or REYATAZ with ritonavir and other hormonal contraceptives (eg, contraceptive patch, contraceptive vaginal ring, or injectable contraceptives) or oral contraceptives containing progestogens other than norethindrone or norgestimate, or less than 25 mcg of ethinyl estradiol, has not been studied; therefore, alternative methods of contraception are recommended.
Immunosuppressants: cyclosporine, sirolimus, tacrolimus | ↑ immunosuppressants | Therapeutic concentration monitoring is recommended for these immunosuppressants when coadministered with REYATAZ.
Inhaled beta agonist: salmeterol | ↑ salmeterol | Coadministration of salmeterol with REYATAZ is not recommended. Concomitant use of salmeterol and REYATAZ may result in increased risk of cardiovascular adverse reactions associated with salmeterol, including QT prolongation, palpitations, and sinus tachycardia.
Inhaled/nasal steroid: fluticasone | REYATAZ ↑ fluticasone | Concomitant use of fluticasone propionate and REYATAZ without ritonavir should be used with caution. Consider alternatives to fluticasone propionate, particularly for long-term use.
 | REYATAZ with ritonavir ↑ fluticasone | With concomitant use of fluticasone propionate and REYATAZ with ritonavir systemic corticosteroid effects, including Cushing’s syndrome and adrenal suppression, have been reported during postmarketing use in patients receiving ritonavir and inhaled or intranasally administered fluticasone propionate. Coadministration of fluticasone propionate and REYATAZ with ritonavir is not recommended unless the potential benefit to the patient outweighs the risk of systemic corticosteroid side effects [see Warnings and Precautions (5.1)].
Macrolide antibiotics: clarithromycin | ↑ clarithromycin ↓ 14-OH clarithromycin ↑ atazanavir | Increased concentrations of clarithromycin may cause QTc prolongations; therefore, a dose reduction of clarithromycin by 50% should be considered when it is coadministered with REYATAZ. In addition, concentrations of the active metabolite 14-OH clarithromycin are significantly reduced; consider alternative therapy for indications other than infections due to Mycobacterium avium complex. Coadministration of REYATAZ with ritonavir and clarithromycin has not been studied.
Opioids: buprenorphine | REYATAZ or; REYATAZ with ritonavir; ↑ buprenorphine ↑ norbuprenorphine | Coadministration of REYATAZ with ritonavir and buprenorphine warrants clinical monitoring for sedation and cognitive effects. A dose reduction of buprenorphine may be considered.
 | REYATAZ; ↓ atazanavir | The coadministration of REYATAZ and buprenorphine without ritonavir is not recommended.
PDE5 inhibitors: sildenafil, tadalafil, vardenafil | ↑ sildenafil ↑ tadalafil ↑ vardenafil | Coadministration with REYATAZ has not been studied but may result in an increase in PDE5 inhibitor-associated adverse reactions, including hypotension, syncope, visual disturbances, and priapism.; Use of PDE5 inhibitors for pulmonary arterial hypertension (PAH):; Coadministration of REYATAZ with REVATIO® (sildenafil) for the treatment of pulmonary hypertension (PAH) is contraindicated [see Contraindications (4)].; The following dose adjustments are recommended for the use of ADCIRCA® (tadalafil) with REYATAZ: Coadministration of ADCIRCA® in patients on REYATAZ (with or without ritonavir):; - For patients receiving REYATAZ (with or without ritonavir) for at least one week, start ADCIRCA® at 20 mg once daily. Increase to 40 mg once daily based on individual tolerability.; Coadministration of REYATAZ (with or without ritonavir) in patients on ADCIRCA®:; - Avoid the use of ADCIRCA® when starting REYATAZ (with or without ritonavir). Stop ADCIRCA® at least 24 hours before starting REYATAZ (with or without ritonavir). At least one week after starting REYATAZ (with or without ritonavir), resume ADCIRCA® at 20 mg once daily. Increase to 40 mg once daily based on individual tolerability.; Use of PDE5 inhibitors for erectile dysfunction:; Use VIAGRA® (sildenafil) with caution at reduced doses of 25 mg every 48 hours with increased monitoring for adverse events. Use CIALIS® (tadalafil) with caution at reduced doses of 10 mg every 72 hours with increased monitoring for adverse events. REYATAZ with ritonavir: Use vardenafil with caution at reduced doses of no more than 2.5 mg every 72 hours with increased monitoring for adverse reactions. REYATAZ: Use vardenafil with caution at reduced doses of no more than 2.5 mg every 24 hours with increased monitoring for adverse reactions.
Proton-pump inhibitors: omeprazole | ↓ atazanavir | Coadministration of REYATAZ with or without ritonavir and omeprazole may result in loss of virologic response and development of resistance.; In HIV-treatment-naive adult patients:; The proton-pump inhibitor (PPI) dose should not exceed a dose comparable to omeprazole 20 mg and must be taken approximately 12 hours prior to the REYATAZ 300 mg with ritonavir 100 mg dose.; In HIV-treatment-experienced adult patients:; Coadministration of REYATAZ with PPIs is not recommended.
a For magnitude of interactions see Clinical Pharmacology, Tables 21 and 22 (12.3).
b See Contraindications (4), Table 6 for orally administered midazolam.
c In combination with atazanavir 300 mg with ritonavir 100 mg once daily.
d In combination with atazanavir 400 mg once daily.

7.4 Drugs with No Observed Interactions with REYATAZ

No clinically significant drug interactions were observed when REYATAZ was coadministered with methadone, fluconazole, acetaminophen, atenolol, or the nucleoside reverse transcriptase inhibitors lamivudine or zidovudine [see Clinical Pharmacology, Tables 21 and 22 (12.3)].

8 USE IN SPECIFIC POPULATIONS

8.1 Pregnancy

Pregnancy Exposure Registry

There is a pregnancy exposure registry that monitors pregnancy outcomes in patients exposed to REYATAZ during pregnancy. Healthcare providers are encouraged to register patients by calling the Antiretroviral Pregnancy Registry (APR) at 1-800-258-4263.

Risk Summary

Atazanavir has been evaluated in a limited number of women during pregnancy. Available human and animal data suggest that atazanavir does not increase the risk of major birth defects overall compared to the background rate [see Data]. In the U.S. general population, the estimated background risk of major birth defects and miscarriage in clinically recognized pregnancies is 2-4% and 15-20%, respectively. No treatment-related malformations were observed in rats and rabbits, for which the atazanavir exposures were 0.7-1.2 times of those at the human clinical dose (300 mg/day atazanavir boosted with 100 mg/day ritonavir). When atazanavir was administered to rats during pregnancy and throughout lactation, reversible neonatal growth retardation was observed [see Data].

Clinical Considerations

Dose Adjustments during Pregnancy and the Postpartum Period

- REYATAZ must be administered with ritonavir in pregnant patients.
- For pregnant patients, no dosage adjustment is required for REYATAZ with the following exceptions:
  - For treatment-experienced pregnant women during the second or third trimester, when REYATAZ is coadministered with either an H2-receptor antagonist or tenofovir DF, REYATAZ 400 mg with ritonavir 100 mg once daily is recommended. There are insufficient data to recommend a REYATAZ dose for use with both an H2-receptor antagonist and tenofovir DF in treatment-experienced pregnant patients.
- No dosage adjustment is required for postpartum patients. However, patients should be closely monitored for adverse events because atazanavir exposures could be higher during the first 2 months after delivery [see Dosage and Administration (2.6) and Clinical Pharmacology (12.3)].

Maternal Adverse Reactions

Cases of lactic acidosis syndrome, sometimes fatal, and symptomatic hyperlactatemia have occurred in pregnant women using REYATAZ in combination with nucleoside analogues, which are associated with an increased risk of lactic acidosis syndrome.

Hyperbilirubinemia occurs frequently in patients who take REYATAZ [see Warnings and Precautions (5.8)], including those who are pregnant [see Data].

Advise pregnant women of the potential risks of lactic acidosis syndrome and hyperbilirubinemia.

Fetal/Neonatal Adverse Reactions

All infants, including neonates exposed to REYATAZ in utero, should be monitored for the development of severe hyperbilirubinemia during the first few days of life [see Data].

Data

Human Data

In Study AI424-182, REYATAZ with ritonavir (300/100 mg or 400/100 mg) coadministered with lamivudine/zidovudine (150 mg/ 300 mg, as fixed-dose product) was administered to 41 pregnant women with HIV-1, during the second or third trimester. Among the 39 women who completed the study, 38 women achieved an HIV-1 RNA less than 50 copies/mL at time of delivery. Six of 20 (30%) women on REYATAZ with ritonavir 300/100 mg and 13 of 21 (62%) women on REYATAZ with ritonavir 400/100 mg experienced hyperbilirubinemia (total bilirubin greater than or equal to 2.6 times ULN). There were no cases of lactic acidosis observed in clinical trial AI424-182.

Atazanavir drug concentrations in fetal umbilical cord blood were approximately 12% to 19% of maternal concentrations. Among the 40 infants born to 40 pregnant women with HIV-1, all had test results that were negative for HIV-1 DNA at the time of delivery and/or during the first 6 months postpartum. All 40 infants received antiretroviral prophylactic treatment containing zidovudine. No evidence of severe hyperbilirubinemia (total bilirubin levels greater than 20 mg/dL) or acute or chronic bilirubin encephalopathy was observed among neonates in this study. However, 10/36 (28%) infants (6 greater than or equal to 38 weeks gestation and 4 less than 38 weeks gestation) had bilirubin levels of 4 mg/dL or greater within the first day of life.

Lack of ethnic diversity was a study limitation. In the study population, 33/40 (83%) infants were Black/African American, who have a lower incidence of neonatal hyperbilirubinemia than Caucasians and Asians. In addition, women with Rh incompatibility were excluded, as well as women who had a previous infant who developed hemolytic disease and/or had neonatal pathologic jaundice (requiring phototherapy).

Additionally, of the 38 infants who had glucose samples collected in the first day of life, 3 had adequately collected serum glucose samples with values of less than 40 mg/dL that could not be attributed to maternal glucose intolerance, difficult delivery, or sepsis.

Based on prospective reports from the APR of approximately 1600 live births following exposure to atazanavir-containing regimens (including 1037 live births in infants exposed in the first trimester and 569 exposed in second/third trimesters), there was no difference between atazanavir, and overall birth defects compared with the background birth defect rate. In the U.S. general population, the estimated background risk of major birth defects in clinically recognized pregnancies is 2-4%.

Animal Data

In animal reproduction studies, there was no evidence of mortality or teratogenicity in offspring born to animals at systemic drug exposure levels (AUC) 0.7 (in rabbits) to 1.2 (in rats) times those observed at the human clinical dose (300 mg/day atazanavir boosted with 100 mg/day ritonavir). In pre- and postnatal development studies in the rat, atazanavir caused neonatal growth retardation during lactation that reversed after weaning. Maternal drug exposure at this dose was 1.3 times the human exposure at the recommended clinical exposure. Minimal maternal toxicity occurred at this exposure level.

8.2 Lactation

Risk Summary

Atazanavir has been detected in human milk. No data are available regarding atazanavir effects on milk production. Atazanavir was present in the milk of lactating rats and was associated with neonatal growth retardation that reversed after weaning.

Potential risks of breastfeeding include: (1) HIV-1 transmission (in infants without HIV-1), (2) developing viral resistance (in infants with HIV-1), and (3) adverse reactions in a breastfed infant similar to those seen in adults.

8.4 Pediatric Use

REYATAZ is indicated in combination with other antiretroviral agents for the treatment of pediatric patients with HIV-1, 3 months of age and older weighing at least 5 kg. REYATAZ is not recommended for use in pediatric patients below the age of 3 months due to the risk of kernicterus [see Indications and Usage (1)]. All REYATAZ contraindications, warnings, and precautions apply to pediatric patients [see Contraindications (4) and Warnings and Precautions (5)].

The safety, pharmacokinetic profile, and virologic response of REYATAZ in pediatric patients at least 3 months of age and older weighing at least 5 kg were established in three open-label, multicenter clinical trials: PACTG 1020A, AI424-451, and AI424-397 [see Clinical Pharmacology (12.3) and Clinical Studies (14.3)]. The safety profile in pediatric patients was generally similar to that observed in adults [see Adverse Reactions (6.1)]. See Dosage and Administration (2.4, 2.5) for dosing recommendations for the use of REYATAZ capsules and REYATAZ oral powder in pediatric patients.

8.5 Geriatric Use

Clinical studies of REYATAZ did not include sufficient numbers of patients aged 65 and over to determine whether they respond differently from younger patients. Based on a comparison of mean single-dose pharmacokinetic values for Cmax and AUC, a dose adjustment based upon age is not recommended. In general, appropriate caution should be exercised in the administration and monitoring of REYATAZ in elderly patients reflecting the greater frequency of decreased hepatic, renal, or cardiac function, and of concomitant disease or other drug therapy.

8.6 Age/Gender

A study of the pharmacokinetics of atazanavir was performed in young (n=29; 18-40 years) and elderly (n=30; ≥65 years) healthy participants. There were no clinically significant pharmacokinetic differences observed due to age or gender.

8.7 Impaired Renal Function

REYATAZ is not recommended for use in treatment-experienced patients with HIV-1, who have end-stage renal disease managed with hemodialysis [see Dosage and Administration (2.7) and Clinical Pharmacology (12.3)].

8.8 Impaired Hepatic Function

REYATAZ is not recommended for use in patients with severe hepatic impairment. REYATAZ with ritonavir is not recommended in patients with any degree of hepatic impairment [see Dosage and Administration (2.8) and Clinical Pharmacology (12.3)].

10 OVERDOSAGE

Human experience of acute overdose with REYATAZ is limited. Single doses up to 1200 mg (three times the 400 mg maximum recommended dose) have been taken by healthy participants without symptomatic untoward effects. A single self-administered overdose of 29.2 g of REYATAZ in a patient with HIV-1 (73 times the 400-mg recommended dose) was associated with asymptomatic bifascicular block and PR interval prolongation. These events resolved spontaneously. At REYATAZ doses resulting in high atazanavir exposures, jaundice due to indirect (unconjugated) hyperbilirubinemia (without associated liver function test changes) or PR interval prolongation may be observed [see Warnings and Precautions (5.1, 5.8) and Clinical Pharmacology (12.2)].

Treatment of overdosage with REYATAZ should consist of general supportive measures, including monitoring of vital signs and ECG, and observations of the patient’s clinical status. If indicated, elimination of unabsorbed atazanavir should be achieved by emesis or gastric lavage. Administration of activated charcoal may also be used to aid removal of unabsorbed drug. There is no specific antidote for overdose with REYATAZ. Since atazanavir is extensively metabolized by the liver and is highly protein bound, dialysis is unlikely to be beneficial in significant removal of this medicine.

11 DESCRIPTION

The active ingredient in REYATAZ capsules and oral powder is atazanavir sulfate, which is an HIV-1 protease inhibitor.

The chemical name for atazanavir sulfate is (3S,8S,9S,12S)-3,12-Bis(1,1-dimethylethyl)-8-hydroxy-4,11-dioxo-9-(phenylmethyl)-6-[[4-(2-pyridinyl)phenyl]methyl]-2,5,6,10,13-pentaazatetradecanedioic acid dimethyl ester, sulfate (1:1). Its molecular formula is C38H52N6O7•H2SO4, which corresponds to a molecular weight of 802.9 (sulfuric acid salt). The free base molecular weight is 704.9. Atazanavir sulfate has the following structural formula:

Atazanavir sulfate is a white to pale-yellow crystalline powder. It is slightly soluble in water (4-5 mg/mL, free base equivalent) with the pH of a saturated solution in water being about 1.9 at 24 ± 3°C.

REYATAZ Capsules are available for oral administration in strengths of 200 mg or 300 mg of atazanavir, which are equivalent to 227.8 mg or 341.69 mg of atazanavir sulfate, respectively. The capsules also contain the following inactive ingredients: crospovidone, lactose monohydrate, and magnesium stearate. The capsule shells contain the following inactive ingredients: gelatin, FD&C Blue No. 2, titanium dioxide, black iron oxide, red iron oxide, and yellow iron oxide. The capsules are printed with ink containing shellac, titanium dioxide, FD&C Blue No. 2, isopropyl alcohol, ammonium hydroxide, propylene glycol, n-butyl alcohol, simethicone, and dehydrated alcohol.

REYATAZ oral powder comes in a packet containing 50 mg of atazanavir equivalent to 56.9 mg of atazanavir sulfate in 1.5 g of powder. The powder is off-white to pale yellow and contains the following inactive ingredients: aspartame, sucrose, and orange-vanilla flavor.

12 CLINICAL PHARMACOLOGY

12.1 Mechanism of Action

Atazanavir is an HIV-1 antiretroviral drug [see Microbiology (12.4)].

12.2 Pharmacodynamics

Cardiac Electrophysiology

Concentration- and dose-dependent prolongation of the PR interval in the electrocardiogram has been observed in healthy participants receiving atazanavir. In placebo-controlled Study AI424-076, the mean (±SD) maximum change in PR interval from the predose value was 24 (±15) msec following oral dosing with 400 mg of atazanavir (n=65) compared to 13 (±11) msec following dosing with placebo (n=67). The PR interval prolongations in this study were asymptomatic. There is limited information on the potential for a pharmacodynamic interaction in humans between atazanavir and other drugs that prolong the PR interval of the electrocardiogram [see Warnings and Precautions (5.1)].

Electrocardiographic effects of atazanavir were determined in a clinical pharmacology study of 72 healthy participants. Oral doses of 400 mg (maximum recommended dosage) and 800 mg (twice the maximum recommended dosage) were compared with placebo; there was no concentration-dependent effect of atazanavir on the QTc interval (using Fridericia’s correction). In 1793 participants with HIV-1, receiving antiretroviral regimens, QTc prolongation was comparable in the atazanavir and comparator regimens. No atazanavir-treated healthy participant or participant with HIV-1 in clinical trials had a QTc interval >500 msec [see Warnings and Precautions (5.1)].

12.3 Pharmacokinetics

The pharmacokinetics of atazanavir were evaluated in adult participants who either were healthy, or with HIV-1, after administration of REYATAZ 400 mg once daily and after administration of REYATAZ 300 mg with ritonavir 100 mg once daily (see Table 17).

Table 17: Steady-State Pharmacokinetics of Atazanavir in Healthy Participants or Participants with HIV-1 in the Fed State
 | 400 mg once daily |  | 300 mg with ritonavir 100 mg once daily
Parameter | Healthy Participants (n=14) | Participants with HIV-1 (n=13) | Healthy Participants (n=28) | Participants with HIV-1 (n=10)
Cmax (ng/mL)
Geometric mean (CV%) | 5199 (26) | 2298 (71) | 6129 (31) | 4422 (58)
Mean (SD) | 5358 (1371) | 3152 (2231) | 6450 (2031) | 5233 (3033)
Tmax (h)
Median | 2.5 | 2.0 | 2.7 | 3.0
AUC (ng•h/mL)
Geometric mean (CV%) | 28132 (28) | 14874 (91) | 57039 (37) | 46073 (66)
Mean (SD) | 29303 (8263) | 22262 (20159) | 61435 (22911) | 53761 (35294)
T-half (h)
Mean (SD) | 7.9 (2.9) | 6.5 (2.6) | 18.1 (6.2)a | 8.6 (2.3)
Cmin (ng/mL)
Geometric mean (CV%) | 159 (88) | 120 (109) | 1227 (53) | 636 (97)
Mean (SD) | 218 (191) | 273 (298)b | 1441 (757) | 862 (838)
a n=26.
b n=12.

Figure 1 displays the mean plasma concentrations of atazanavir at steady state after REYATAZ 400 mg once daily (as two 200-mg capsules) with a light meal and after REYATAZ 300 mg (as two 150-mg capsules) with ritonavir 100 mg once daily with a light meal in adult participants with HIV-1.

Figure 1: Mean (SD) Steady-State Plasma Concentrations of Atazanavir 400 mg (n=13) and 300 mg with Ritonavir (n=10) for Adult Participants with HIV-1

Absorption

Atazanavir is rapidly absorbed with a Tmax of approximately 2.5 hours. Atazanavir demonstrates nonlinear pharmacokinetics with greater than dose-proportional increases in AUC and Cmax values over the dose range of 200 to 800 mg once daily. Steady state is achieved between Days 4 and 8, with an accumulation of approximately 2.3-fold.

Food Effect

Administration of REYATAZ with food enhances bioavailability and reduces pharmacokinetic variability. Administration of a single 400-mg dose of REYATAZ with a light meal (357 kcal, 8.2 g fat, 10.6 g protein) resulted in a 70% increase in AUC and 57% increase in Cmax relative to the fasting state. Administration of a single 400-mg dose of REYATAZ with a high-fat meal (721 kcal, 37.3 g fat, 29.4 g protein) resulted in a mean increase in AUC of 35% with no change in Cmax relative to the fasting state. Administration of REYATAZ with either a light meal or high-fat meal decreased the coefficient of variation of AUC and Cmax by approximately one-half compared to the fasting state.

Coadministration of a single 300-mg dose of REYATAZ and a 100-mg dose of ritonavir with a light meal (336 kcal, 5.1 g fat, 9.3 g protein) resulted in a 33% increase in the AUC and a 40% increase in both the Cmax and the 24-hour concentration of atazanavir relative to the fasting state. Coadministration with a high-fat meal (951 kcal, 54.7 g fat, 35.9 g protein) did not affect the AUC of atazanavir relative to fasting conditions and the Cmax was within 11% of fasting values. The 24-hour concentration following a high-fat meal was increased by approximately 33% due to delayed absorption; the median Tmax increased from 2.0 to 5.0 hours. Coadministration of REYATAZ with ritonavir with either a light or a high-fat meal decreased the coefficient of variation of AUC and Cmax by approximately 25% compared to the fasting state.

Distribution

Atazanavir is 86% bound to human serum proteins and protein binding is independent of concentration. Atazanavir binds to both alpha-1-acid glycoprotein (AAG) and albumin to a similar extent (89% and 86%, respectively). In a multiple-dose study in participants with HIV-1 dosed with REYATAZ 400 mg once daily with a light meal for 12 weeks, atazanavir was detected in the cerebrospinal fluid and semen. The cerebrospinal fluid/plasma ratio for atazanavir (n=4) ranged between 0.0021 and 0.0226 and seminal fluid/plasma ratio (n=5) ranged between 0.11 and 4.42.

Metabolism

Atazanavir is extensively metabolized in humans. The major biotransformation pathways of atazanavir in humans consisted of monooxygenation and dioxygenation. Other minor biotransformation pathways for atazanavir or its metabolites consisted of glucuronidation, N-dealkylation, hydrolysis, and oxygenation with dehydrogenation. Two minor metabolites of atazanavir in plasma have been characterized. Neither metabolite demonstrated in vitro antiviral activity. In vitro studies using human liver microsomes suggested that atazanavir is metabolized by CYP3A.

Elimination

Following a single 400-mg dose of ^14C-atazanavir, 79% and 13% of the total radioactivity was recovered in the feces and urine, respectively. Unchanged drug accounted for approximately 20% and 7% of the administered dose in the feces and urine, respectively. The mean elimination half-life of atazanavir in healthy participants (n=214) and adult participants with HIV-1 (n=13) was approximately 7 hours at steady state following a dose of 400 mg daily with a light meal.

Specific Populations

Renal Impairment

In healthy participants, the renal elimination of unchanged atazanavir was approximately 7% of the administered dose. REYATAZ has been studied in adult participants with severe renal impairment (n=20), including those on hemodialysis, at multiple doses of 400 mg once daily. The mean atazanavir Cmax was 9% lower, AUC was 19% higher, and Cmin was 96% higher in participants with severe renal impairment not undergoing hemodialysis (n=10), than in age-, weight-, and gender-matched participants with normal renal function. In a 4-hour dialysis session, 2.1% of the administered dose was removed. When atazanavir was administered either prior to, or following hemodialysis (n=10), the geometric means for Cmax, AUC, and Cmin were approximately 25% to 43% lower compared to participants with normal renal function. The mechanism of this decrease is unknown. REYATAZ is not recommended for use in treatment-experienced patients with HIV-1 who have end-stage renal disease managed with hemodialysis [see Dosage and Administration (2.7)].

Hepatic Impairment

REYATAZ has been studied in adult participants with moderate-to-severe hepatic impairment (14 with Child-Pugh B and 2 with Child-Pugh C) after a single 400-mg dose. The mean AUC(0-∞) was 42% greater in participants with impaired hepatic function than in healthy participants. The mean half-life of atazanavir in hepatically impaired participants was 12.1 hours compared to 6.4 hours in healthy participants. A dose reduction to 300 mg is recommended for patients with moderate hepatic impairment (Child-Pugh Class B) who have not experienced prior virologic failure as increased concentrations of atazanavir are expected. REYATAZ is not recommended for use in patients with severe hepatic impairment. The pharmacokinetics of REYATAZ in combination with ritonavir has not been studied in participants with hepatic impairment; thus, coadministration of REYATAZ with ritonavir is not recommended for use in patients with any degree of hepatic impairment [see Dosage and Administration (2.8)].

Pediatrics

The pharmacokinetic parameters for atazanavir at steady state in pediatric participants taking the powder formulation are summarized in Table 18 by weight ranges [see Dosage and Administration (2.5)].

Table 18: Steady-State Pharmacokinetics of Atazanavir (powder formulation) with Ritonavir in Pediatric Participants with HIV-1
Body Weight (range in kg) [n] | atazanavir with ritonavir Dose (mg) | Cmax ng/mL Geometric Mean (CV%) | AUC ng•h/mL Geometric Mean (CV%) | Cmin ng/mL Geometric Mean (CV%)
5 to <10 [20] | 150/80 | 4131 (55%) | 32503 (61%) | 336 (76%)
5 to <10 [10] | 200/80 | 4466 (59%) | 39519 (54%) | 550 (60%)
10 to <15 [18] | 200/80 | 5197 (53%) | 50305 (67%) | 572 (111%)
15 to <25 [32] | 250/80 | 5394 (46%) | 55687 (45%) | 686 (68%)
25 to <35 [8] | 300/100 | 4209 (52%) | 44329 (63%) | 468 (104%)

The pharmacokinetic parameters for atazanavir at steady state in pediatric participants taking the capsule formulation were predicted by a population pharmacokinetic model and are summarized in Table 19 by weight ranges that correspond to the recommended doses [see Dosage and Administration (2.4)].

Table 19: Predicted Steady-State Pharmacokinetics of Atazanavir (capsule formulation) with Ritonavir in Pediatric Participants with HIV-1
Body Weight (range in kg) | atazanavir with ritonavir Dose (mg) | Cmax ng/mL Geometric Mean (CV%) | AUC ng•h/mL Geometric Mean (CV%) | Cmin ng/mL Geometric Mean (CV%)
15 to <35 | 200/100 | 3303 (86%) | 37235 (84%) | 538 (99%)
≥35 | 300/100 | 2980 (82%) | 37643 (83%) | 653 (89%)

Pregnancy

The pharmacokinetic data from pregnant women with HIV-1 receiving REYATAZ Capsules with ritonavir are presented in Table 20.

Table 20: Steady-State Pharmacokinetics of Atazanavir with Ritonavir in Pregnant Women with HIV-1 in the Fed State
 | Atazanavir 300 mg with ritonavir 100 mg
Pharmacokinetic Parameter | 2nd Trimester (n=5a) | 3rd Trimester (n=20) | Postpartumb (n=34)
Cmax ng/mL; Geometric mean (CV%) | 3078.85; (50) | 3291.46; (48) | 5721.21; (31)
AUC ng•h/mL; Geometric mean (CV%) | 27657.1; (43) | 34251.5; (43) | 61990.4; (32)
Cmin ng/mLc; Geometric mean (CV%) | 538.70; (46) | 668.48; (50) | 1462.59; (45)
a Available data during the 2nd trimester are limited.
b Atazanavir peak concentrations and AUCs were found to be approximately 28% to 43% higher during the postpartum period (4-12 weeks) than those observed historically in, non-pregnant patients with HIV-1. Atazanavir plasma trough concentrations were approximately 2.2-fold higher during the postpartum period when compared to those observed historically in non-pregnant patients with HIV-1.
c Cmin is concentration 24 hours post-dose.

Drug Interaction Data

Atazanavir is a metabolism-dependent CYP3A inhibitor, with a Kinact value of 0.05 to 0.06 min^−1 and Ki value of 0.84 to 1.0 µM. Atazanavir is also a direct inhibitor for UGT1A1 (Ki=1.9 µM) and CYP2C8 (Ki=2.1 µM).

Atazanavir has been shown in vivo not to induce its own metabolism nor to increase the biotransformation of some drugs metabolized by CYP3A. In a multiple-dose study, REYATAZ decreased the urinary ratio of endogenous 6β-OH cortisol to cortisol versus baseline, indicating that CYP3A production was not induced.

Clinically significant interactions are not expected between atazanavir and substrates of CYP2C19, CYP2C9, CYP2D6, CYP2B6, CYP2A6, CYP1A2, or CYP2E1. Clinically significant interactions are not expected between atazanavir when administered with ritonavir and substrates of CYP2C8. See the complete prescribing information for ritonavir for information on other potential drug interactions with ritonavir.

Based on known metabolic profiles, clinically significant drug interactions are not expected between REYATAZ and dapsone, trimethoprim/sulfamethoxazole, azithromycin, or erythromycin. REYATAZ does not interact with substrates of CYP2D6 (eg, nortriptyline, desipramine, metoprolol).

Drug interaction studies were performed with REYATAZ and other drugs likely to be coadministered and some drugs commonly used as probes for pharmacokinetic interactions. The effects of coadministration of REYATAZ on the AUC, Cmax, and Cmin are summarized in Tables 21 and 22. Neither didanosine EC nor diltiazem had a significant effect on atazanavir exposures (see Table 22 for effect of atazanavir on didanosine EC or diltiazem exposures). REYATAZ did not have a significant effect on the exposures of didanosine (when administered as the buffered tablet), stavudine, or fluconazole. For information regarding clinical recommendations, see Drug Interactions (7).

Table 21: Drug Interactions: Pharmacokinetic Parameters for Atazanavir in the Presence of Coadministered Drugsa
Coadministered Drug | Coadministered Drug Dose/Schedule | REYATAZ Dose/Schedule | Ratio (90% Confidence Interval) of Atazanavir Pharmacokinetic Parameters with/without Coadministered Drug; No Effect = 1.00
Coadministered Drug | Coadministered Drug Dose/Schedule | REYATAZ Dose/Schedule | Cmax | AUC | Cmin
atenolol | 50 mg QD, d 7–11 (n=19) and d 19–23 | 400 mg QD, d 1–11 (n=19) | 1.00 (0.89, 1.12) | 0.93 (0.85, 1.01) | 0.74 (0.65, 0.86)
clarithromycin | 500 mg BID, d 7–10 (n=29) and d 18–21 | 400 mg QD, d 1–10 (n=29) | 1.06 (0.93, 1.20) | 1.28 (1.16, 1.43) | 1.91 (1.66, 2.21)
didanosine (ddI) (buffered tablets) and stavudine (d4T)b | ddI: 200 mg × 1 dose, d4T: 40 mg × 1 dose (n=31) | 400 mg × 1 dose simultaneously with ddI and d4T (n=31) | 0.11 (0.06, 0.18) | 0.13 (0.08, 0.21) | 0.16 (0.10, 0.27)
 | ddI: 200 mg × 1 dose, d4T: 40 mg × 1 dose (n=32) | 400 mg × 1 dose 1 h after ddI + d4T (n=32) | 1.12 (0.67, 1.18) | 1.03 (0.64, 1.67) | 1.03 (0.61, 1.73)
efavirenz | 600 mg QD, d 7–20 (n=27) | 400 mg QD, d 1–20 (n=27) | 0.41 (0.33, 0.51) | 0.26 (0.22, 0.32) | 0.07 (0.05, 0.10)
 | 600 mg QD, d 7–20; (n=13) | 400 mg QD, d 1–6 (n=23) then 300 mg with ritonavir 100 mg QD, 2 h before efavirenz, d 7–20 (n=13) | 1.14 (0.83, 1.58) | 1.39 (1.02, 1.88) | 1.48 (1.24, 1.76)
 | 600 mg QD, d 11–24 (pm) (n=14) | 300 mg QD with ritonavir 100 mg QD, d 1–10 (pm) (n=22), then 400 mg QD with ritonavir 100 mg QD, d 11–24 (pm), (simultaneously with efavirenz) (n=14) | 1.17 (1.08, 1.27) | 1.00 (0.91, 1.10) | 0.58 (0.49, 0.69)
famotidine | 40 mg BID, d 7–12 (n=15) | 400 mg QD, d 1–6 (n=45), d 7–12 (simultaneous administration) (n=15) | 0.53 (0.34, 0.82) | 0.59 (0.40, 0.87) | 0.58 (0.37, 0.89)
 | 40 mg BID, d 7–12 (n=14) | 400 mg QD (pm), d 1–6 (n=14), d 7–12 (10 h after, 2 h before famotidine) (n=14) | 1.08 (0.82, 1.41) | 0.95 (0.74, 1.21) | 0.79 (0.60, 1.04)
 | 40 mg BID, d 11–20 (n=14)c | 300 mg QD with ritonavir 100 mg QD, d 1–10 (n=46), d 11–20d (simultaneous administration) (n=14) | 0.86 (0.79, 0.94) | 0.82 (0.75, 0.89) | 0.72 (0.64, 0.81)
 | 20 mg BID, d 11–17 (n=18) | 300 mg QD with ritonavir 100 mg QD and tenofovir DF 300 mg QD, d 1–10 (am) (n=39), d 11–17 (am) (simultaneous administration with am famotidine) (n=18)d,e | 0.91 (0.84, 0.99) | 0.90 (0.82, 0.98) | 0.81 (0.69, 0.94)
 | 40 mg QD (pm), d 18–24 (n=20) | 300 mg QD with ritonavir 100 mg QD and tenofovir DF 300 mg QD, d 1–10 (am) (n=39), d 18–24 (am) (12 h after pm famotidine) (n=20)e | 0.89 (0.81, 0.97) | 0.88 (0.80, 0.96) | 0.77 (0.63, 0.93)
 | 40 mg BID, d 18–24 (n=18) | 300 mg QD with ritonavir 100 mg QD and tenofovir DF 300 mg QD, d 1–10 (am) (n=39), d 18–24 (am) (10 h after pm famotidine and 2 h before am famotidine) (n=18)e | 0.74 (0.66, 0.84) | 0.79 (0.70, 0.88) | 0.72 (0.63, 0.83)
 | 40 mg BID, d 11–20 (n=15) | 300 mg QD with ritonavir 100 mg QD, d 1–10 (am) (n=46), then 400 mg QD with ritonavir 100 mg QD, d 11–20 (am) (n=15) | 1.02 (0.87, 1.18) | 1.03 (0.86, 1.22) | 0.86 (0.68, 1.08)
grazoprevir/elbasvir | grazoprevir 200 mg QD d 1–35 (n = 11) | 300 mg QD with ritonavir 100 mg QD, d 1–35 (n = 11) | 1.12 (1.01, 1.24) | 1.43 (1.30, 1.57) | 1.23 (1.13, 1.34)
grazoprevir/elbasvir | elbasvir 50 mg QD d 1–35 (n = 8) | 300 mg QD with ritonavir 100 mg QD, d 1–35 (n = 8) | 1.02 (0.96, 1.08) | 1.07 (0.98,1.17) | 1.15 (1.02, 1.29)
ketoconazole | 200 mg QD, d 7–13 (n=14) | 400 mg QD, d 1–13 (n=14) | 0.99 (0.77, 1.28) | 1.10 (0.89, 1.37) | 1.03 (0.53, 2.01)
nevirapinef,g | 200 mg BID, d 1–23 (n=23) | 300 mg QD with ritonavir 100 mg QD, d 4–13, then 400 mg QD with ritonavir 100 mg QD, d 14–23 (n=23)h | 0.72 (0.60, 0.86) 1.02 (0.85, 1.24) | 0.58 (0.48, 0.71) 0.81 (0.65, 1.02) | 0.28 (0.20, 0.40) 0.41 (0.27, 0.60)
omeprazole | 40 mg QD, d 7–12 (n=16)i | 400 mg QD, d 1–6 (n=48), d 7–12 (n=16) | 0.04 (0.04, 0.05) | 0.06 (0.05, 0.07) | 0.05 (0.03, 0.07)
 | 40 mg QD, d 11 –20 (n=15)i | 300 mg QD with ritonavir 100 mg QD, d 1–20 (n=15) | 0.28 (0.24, 0.32) | 0.24 (0.21, 0.27) | 0.22 (0.19, 0.26)
 | 20 mg QD, d 17–23 (am) (n=13) | 300 mg QD with ritonavir 100 mg QD, d 7–16 (pm) (n=27), d 17–23 (pm) (n=13)j,k | 0.61 (0.46, 0.81) | 0.58 (0.44, 0.75) | 0.54 (0.41, 0.71)
 | 20 mg QD, d 17–23 (am) (n=14) | 300 mg QD with ritonavir 100 mg QD, d 7–16 (am) (n=27), then 400 mg QD with ritonavir 100 mg QD, d 17–23 (am) (n=14)l,m | 0.69 (0.58, 0.83) | 0.70 (0.57, 0.86) | 0.69 (0.54, 0.88)
pitavastatin | 4 mg QD; for 5 days | 300 mg QD for 5 days | 1.13 (0.96, 1.32) | 1.06 (0.90, 1.26) | NA
rifabutin | 150 mg QD, d 15–28 (n=7) | 400 mg QD, d 1–28 (n=7) | 1.34 (1.14, 1.59) | 1.15 (0.98, 1.34) | 1.13 (0.68, 1.87)
rifampin | 600 mg QD, d 17–26 (n=16) | 300 mg QD with ritonavir 100 mg QD, d 7–16 (n=48), d 17–26 (n=16) | 0.47 (0.41, 0.53) | 0.28 (0.25, 0.32) | 0.02 (0.02, 0.03)
ritonavirn | 100 mg QD, d 11–20 (n=28) | 300 mg QD, d 1–20 (n=28) | 1.86 (1.69, 2.05) | 3.38 (3.13, 3.63) | 11.89 (10.23, 13.82)
tenofovir DFo | 300 mg QD, d 9–16 (n=34) | 400 mg QD, d 2–16 (n=34) | 0.79; (0.73, 0.86) | 0.75; (0.70, 0.81) | 0.60; (0.52, 0.68)
 | 300 mg QD, d 15–42 (n=10) | 300 mg with ritonavir 100 mg QD, d 1–42 (n=10) | 0.72p (0.50, 1.05) | 0.75p (0.58, 0.97) | 0.77p (0.54, 1.10)
voriconazole (Participants with at least one functional CYP2C19 allele) | 200 mg BID, d 2–3, 22–30; 400 mg BID, d 1, 21 (n=20) | 300 mg with ritonavir 100 mg QD, d 11–30 (n=20) | 0.87 (0.80, 0.96) | 0.88 (0.82, 0.95) | 0.80 (0.72, 0.90)
voriconazole (Participants without a functional CYP2C19 allele) | 50 mg BID, d 2–3, 22–30; 100 mg BID, d 1, 21 (n=8) | 300 mg with ritonavir 100 mg QD, d 11–30 (n=8) | 0.81 (0.66, 1.00) | 0.80 (0.65, 0.97) | 0.69 (0.54, 0.87)

a Data provided are under fed conditions unless otherwise noted.
b All drugs were given under fasted conditions.
c REYATAZ 300 mg with ritonavir 100 mg once daily coadministered with famotidine 40 mg twice daily resulted in atazanavir geometric mean Cmax that was similar and AUC and Cmin values that were 1.79- and 4.46-fold higher relative to REYATAZ 400 mg once daily alone.
d Similar results were noted when famotidine 20 mg BID was administered 2 hours after and 10 hours before atazanavir 300 mg with ritonavir 100 mg and tenofovir DF 300 mg.
e Coadministration of atazanavir with ritonavir and tenofovir DF was administered after a light meal.
f Study was conducted in participants with HIV-1.
g Compared with atazanavir 400 mg historical data without nevirapine (n=13), the ratio of geometric means (90% confidence intervals) for Cmax, AUC, and Cmin were 1.42 (0.98, 2.05), 1.64 (1.11, 2.42), and 1.25 (0.66, 2.36), respectively, for atazanavir with ritonavir 300/100 mg; and 2.02 (1.42, 2.87), 2.28 (1.54, 3.38), and 1.80 (0.94, 3.45), respectively, for atazanavir with ritonavir 400/100 mg.
h Parallel group design; n=23 for atazanavir with ritonavir and nevirapine, n=22 for atazanavir 300 mg/ritonavir 100 mg without nevirapine. Participants were treated with nevirapine prior to study entry.
i Omeprazole 40 mg was administered on an empty stomach 2 hours before REYATAZ.
j Omeprazole 20 mg was administered 30 minutes prior to a light meal in the morning and REYATAZ 300 mg with ritonavir 100 mg in the evening after a light meal, separated by 12 hours from omeprazole.
k REYATAZ 300 mg with ritonavir 100 mg once daily separated by 12 hours from omeprazole 20 mg daily resulted in increases in atazanavir geometric mean AUC (10%) and Cmin (2.4-fold), with a decrease in Cmax (29%) relative to REYATAZ 400 mg once daily in the absence of omeprazole (study days 1–6).
l Omeprazole 20 mg was given 30 minutes prior to a light meal in the morning and REYATAZ 400 mg with ritonavir 100 mg once daily after a light meal, 1 hour after omeprazole. Effects on atazanavir concentrations were similar when REYATAZ 400 mg with ritonavir 100 mg was separated from omeprazole 20 mg by 12 hours.
m REYATAZ 400 mg with ritonavir 100 mg once daily administered with omeprazole 20 mg once daily resulted in increases in atazanavir geometric mean AUC (32%) and Cmin (3.3-fold), with a decrease in Cmax (26%) relative to REYATAZ 400 mg once daily in the absence of omeprazole (study days 1–6).
n Compared with atazanavir 400 mg QD historical data, administration of atazanavir with ritonavir 300/100 mg QD increased the atazanavir geometric mean values of Cmax, AUC, and Cmin by 18%, 103%, and 671%, respectively.
o Note that similar results were observed in studies where administration of tenofovir DF and REYATAZ was separated by 12 hours.
p Ratio of atazanavir with ritonavir and tenofovir DF to atazanavir with ritonavir. Atazanavir 300 mg with ritonavir 100 mg results in higher atazanavir exposure than atazanavir 400 mg (see footnote o). The geometric mean values of atazanavir pharmacokinetic parameters when coadministered with ritonavir and tenofovir DF were: Cmax = 3190 ng/mL, AUC = 34459 ng•h/mL, and Cmin = 491 ng/mL. Study was conducted in participants with HIV-1.
NA = not available.

Table 22: Drug Interactions: Pharmacokinetic Parameters for Coadministered Drugs in the Presence of REYATAZa
Coadministered Drug | Coadministered Drug Dose/Schedule | REYATAZ Dose/Schedule | Ratio (90% Confidence Interval) of Coadministered Drug Pharmacokinetic Parameters with/without REYATAZ; No Effect = 1.00
Coadministered Drug | Coadministered Drug Dose/Schedule | REYATAZ Dose/Schedule | Cmax | AUC | Cmin
acetaminophen | 1 g BID, d 1–20 (n=10) | 300 mg QD with ritonavir 100 mg QD, d 11–20 (n=10) | 0.87 (0.77, 0.99) | 0.97 (0.91, 1.03) | 1.26 (1.08, 1.46)
atenolol | 50 mg QD, d 7–11 (n=19) and d 19–23 | 400 mg QD, d 1–11 (n=19) | 1.34 (1.26, 1.42) | 1.25 (1.16, 1.34) | 1.02 (0.88, 1.19)
clarithromycin | 500 mg BID, d 7–10 (n=21) and d 18–21 | 400 mg QD, d 1–10 (n=21) | 1.50 (1.32, 1.71) OH-clarithromycin: 0.28 (0.24, 0.33) | 1.94 (1.75, 2.16) OH-clarithromycin: 0.30 (0.26, 0.34) | 2.60 (2.35, 2.88) OH-clarithromycin: 0.38 (0.34, 0.42)
ddI (enteric-coated [EC] capsules)b | 400 mg d 1 (fasted), d 8 (fed) (n=34) | 400 mg QD, d 2–8 (n=34) | 0.64 (0.55, 0.74) | 0.66 (0.60, 0.74) | 1.13 (0.91, 1.41)
 | 400 mg d 1 (fasted), d 19 (fed) (n=31) | 300 mg QD with ritonavir 100 mg QD, d 9–19 (n=31) | 0.62 (0.52, 0.74) | 0.66 (0.59, 0.73) | 1.25 (0.92, 1.69)
diltiazem | 180 mg QD, d 7–11 (n=28) and d 19–23 | 400 mg QD, d 1–11 (n=28) | 1.98 (1.78, 2.19) desacetyl-diltiazem: 2.72 (2.44, 3.03) | 2.25 (2.09, 2.16) desacetyl-diltiazem: 2.65 (2.45, 2.87) | 2.42 (2.14, 2.73) desacetyl-diltiazem: 2.21 (2.02, 2.42)
ethinyl estradiol & norethindronec | Ortho-Novum® 7/7/7 QD, d 1–29 (n=19) | 400 mg QD, d 16–29 (n=19) | ethinyl estradiol: 1.15 (0.99, 1.32) norethindrone: 1.67 (1.42, 1.96) | ethinyl estradiol: 1.48 (1.31, 1.68) norethindrone: 2.10 (1.68, 2.62) | ethinyl estradiol: 1.91 (1.57, 2.33) norethindrone: 3.62 (2.57, 5.09)
ethinyl estradiol & norgestimated | Ortho Tri-Cyclen® QD, d 1–28 (n=18), then Ortho Tri-Cyclen® LO QD, d 29–42e (n=14) | 300 mg QD with ritonavir 100 mg QD, d 29–42 (n=14) | ethinyl estradiol: 0.84 (0.74, 0.95) 17-deacetyl norgestimate:f 1.68 (1.51, 1.88) | ethinyl estradiol: 0.81 (0.75, 0.87) 17-deacetyl norgestimate:f 1.85 (1.67, 2.05) | ethinyl estradiol: 0.63 (0.55, 0.71) 17-deacetyl norgestimate:f 2.02 (1.77, 2.31)
glecaprevir/ pibrentasvir | 300 mg glecaprevir (n=12) | 300 mg QD with ritonavir 100 mg QD (n=12) | ≥4.06g (3.15, 5.23) | ≥6.53g (5.24, 8.14) | ≥14.3g (9.85, 20.7)
glecaprevir/ pibrentasvir | 120 mg pibrentasvir (n=12) | 300 mg QD with ritonavir 100 mg QD (n=12) | ≥1.29g (1.15, 1.45) | ≥1.64g (1.48, 1.82) | ≥2.29g (1.95, 2.68)
grazoprevir/elbasvir | grazoprevir 200 mg QD d 1–35 (n=12) | 300 mg QD with ritonavir 100 mg QD d 1–35 (n=12) | 6.24 (4.42, 8.81) | 10.58 (7.78, 14.39) | 11.64 (7.96, 17.02)
grazoprevir/elbasvir | elbasvir 50 mg QD d 1–35 (n=10) | 300 mg QD with ritonavir 100 mg QD d 1–35 (n=10) | 4.15 (3.46, 4.97) | 4.76 (4.07, 5.56) | 6.45 (5.51, 7.54)
methadone | Stable maintenance; dose, d 1–15 (n=16) | 400 mg QD, d 2–15 (n=16) | (R)-methadoneh 0.91 (0.84, 1.0) total: 0.85 (0.78, 0.93) | (R)-methadoneh 1.03 (0.95, 1.10) total: 0.94 (0.87, 1.02) | (R)-methadoneh 1.11 (1.02, 1.20) total: 1.02 (0.93, 1.12)
nevirapinei,j | 200 mg BID, d 1–23 (n=23) | 300 mg QD with ritonavir 100 mg QD, d 4–13, then 400 mg QD with ritonavir 100 mg QD, d 14–23 (n=23) | 1.17 (1.09, 1.25) 1.21 (1.11, 1.32) | 1.25 (1.17, 1.34) 1.26 (1.17, 1.36) | 1.32 (1.22, 1.43) 1.35 (1.25, 1.47)
omeprazolek | 40 mg single dose, d 7 and d 20 (n=16) | 400 mg QD, d 1–12 (n=16) | 1.24 (1.04, 1.47) | 1.45 (1.20, 1.76) | NA
rifabutin | 300 mg QD, d 1–10 then 150 mg QD, d 11–20 (n=3) | 600 mg QD,l d 11–20 (n=3) | 1.18 (0.94, 1.48) 25-O-desacetyl-rifabutin: 8.20 (5.90, 11.40) | 2.10 (1.57, 2.79) 25-O-desacetyl-rifabutin: 22.01 (15.97, 30.34) | 3.43 (1.98, 5.96) 25-O-desacetyl-rifabutin: 75.6 (30.1, 190.0)
 | 150 mg twice weekly, d 1–15 (n=7) | 300 mg QD with ritonavir 100 mg QD, d 1–17 (n=7) | 2.49m (2.03, 3.06) 25-O-desacetyl-rifabutin: 7.77 (6.13, 9.83) | 1.48m (1.19, 1.84) 25-O-desacetyl-rifabutin: 10.90 (8.14, 14.61) | 1.40m (1.05, 1.87) 25-O-desacetyl-rifabutin: 11.45 (8.15, 16.10)
pitavastatin | 4 mg QD for 5 days | 300 mg QD for 5 days | 1.60 (1.39, 1.85) | 1.31 (1.23, 1.39) | NA
rosiglitazonen | 4 mg single dose, d 1, 7, 17 (n=14) | 400 mg QD, d 2–7, then 300 mg QD with ritonavir 100 mg QD, d 8–17 (n=14) | 1.08 (1.03, 1.13) 0.97 (0.91, 1.04) | 1.35 (1.26, 1.44) 0.83 (0.77, 0.89) | NA NA
rosuvastatin | 10 mg single dose | 300 mg QD with ritonavir 100 mg QD for 7 days | ↑ 7-foldo | ↑ 3-foldo | NA
saquinavirp (soft gelatin capsules) | 1200 mg QD, d 1–13 (n=7) | 400 mg QD, d 7–13 (n=7) | 4.39 (3.24, 5.95) | 5.49 (4.04, 7.47) | 6.86 (5.29, 8.91)
sofosbuvir/ velpatasvir/ voxilaprevir | 400 mg sofosbuvir single dose (n=15) | 300 mg with 100 mg ritonavir single dose (n=15) | 1.29 (1.09, 1.52) sofosbuvir metabolite GS-331007 1.05 (0.99, 1.12) | 1.40 (1.25, 1.57) sofosbuvir metabolite GS-331007 1.25 (1.16, 1.36) | NA
sofosbuvir/ velpatasvir/ voxilaprevir | 100 mg velpatasvir single dose (n=15) | 300 mg with 100 mg ritonavir single dose (n=15) | 1.29 (1.07, 1.56) | 1.93 (1.58, 2.36) | NA
sofosbuvir/ velpatasvir/ voxilaprevir | 100 mg voxilaprevir single dose (n=15) | 300 mg with 100 mg ritonavir single dose (n=15) | 4.42 (3.65, 5.35) | 4.31 (3.76, 4.93) | NA
tenofovir DFq | 300 mg QD, d 9–16 (n=33) and d 24–30 (n=33) | 400 mg QD, d 2–16 (n=33) | 1.14 (1.08, 1.20) | 1.24 (1.21, 1.28) | 1.22 (1.15, 1.30)
 | 300 mg QD, d 1–7 (pm) (n=14) d 25–34 (pm) (n=12) | 300 mg QD with ritonavir 100 mg QD, d 25–34 (am) (n=12)r | 1.34 (1.20, 1.51) | 1.37 (1.30, 1.45) | 1.29 (1.21, 1.36)
voriconazole (Participants with at least one functional CYP2C19 allele) | 200 mg BID, d 2–3, 22–30; 400 mg BID, d 1, 21 (n=20) | 300 mg with ritonavir 100 mg QD, d 11–30 (n=20) | 0.90 (0.78, 1.04) | 0.67 (0.58, 0.78) | 0.61 (0.51, 0.72)
voriconazole (Participants without a functional CYP2C19 allele) | 50 mg BID, d 2–3, 22–30; 100 mg BID, d 1, 21 (n=8) | 300 mg with ritonavir 100 mg QD, d 11–30 (n=8) | 4.38 (3.55, 5.39) | 5.61 (4.51, 6.99) | 7.65 (5.71, 10.2)
lamivudine and zidovudine | 150 mg lamivudine and 300 mg zidovudine BID, d 1–12 (n=19) | 400 mg QD, d 7–12 (n=19) | lamivudine: 1.04 (0.92, 1.16) zidovudine: 1.05 (0.88, 1.24) zidovudine glucuronide: 0.95 (0.88, 1.02) | lamivudine: 1.03 (0.98, 1.08) zidovudine: 1.05 (0.96, 1.14) zidovudine glucuronide: 1.00 (0.97, 1.03) | lamivudine: 1.12 (1.04, 1.21) zidovudine: 0.69 (0.57, 0.84) zidovudine glucuronide: 0.82 (0.62, 1.08)
a Data provided are under fed conditions unless otherwise noted.
b 400 mg ddI EC and REYATAZ were administered together with food on Days 8 and 19.
c Upon further dose normalization of ethinyl estradiol 25 mcg with atazanavir relative to ethinyl estradiol 35 mcg without atazanavir, the ratio of geometric means (90% confidence intervals) for Cmax, AUC, and Cmin were 0.82 (0.73, 0.92), 1.06 (0.95, 1.17), and 1.35 (1.11, 1.63), respectively.
d Upon further dose normalization of ethinyl estradiol 35 mcg with atazanavir with ritonavir relative to ethinyl estradiol 25 mcg without atazanavir with ritonavir, the ratio of geometric means (90% confidence intervals) for Cmax, AUC, and Cmin were 1.17 (1.03, 1.34), 1.13 (1.05, 1.22), and 0.88 (0.77, 1.00), respectively.
e All participants were on a 28-day lead-in period; one full cycle of Ortho Tri-Cyclen®. Ortho Tri-Cyclen® contains 35 mcg of ethinyl estradiol. Ortho Tri-Cyclen® LO contains 25 mcg of ethinyl estradiol. Results were dose normalized to an ethinyl estradiol dose of 35 mcg.
f 17-deacetyl norgestimate is the active component of norgestimate.
g Effect of atazanavir with ritonavir on the first dose of glecaprevir and pibrentasvir is reported.
h (R)-methadone is the active isomer of methadone.
i Study was conducted in participants with HIV-1.
j Participants were treated with nevirapine prior to study entry.
k Omeprazole was used as a metabolic probe for CYP2C19. Omeprazole was given 2 hours after REYATAZ on Day 7; and was given alone 2 hours after a light meal on Day 20.
l Not the recommended therapeutic dose of atazanavir.
m When compared to rifabutin 150 mg QD alone d1–10 (n=14). Total of rifabutin and 25-O-desacetyl-rifabutin: AUC 2.19 (1.78, 2.69).
n Rosiglitazone used as a probe substrate for CYP2C8.
o Mean ratio (with/without coadministered drug). ↑ indicates an increase in rosuvastatin exposure.
p The combination of atazanavir and saquinavir 1200 mg QD produced daily saquinavir exposures similar to the values produced by the standard therapeutic dosing of saquinavir at 1200 mg TID. However, the Cmax is about 79% higher than that for the standard dosing of saquinavir (soft gelatin capsules) alone at 1200 mg TID.
q Note that similar results were observed in a study where administration of tenofovir DF and REYATAZ was separated by 12 hours.
r Administration of tenofovir DF and REYATAZ was temporally separated by 12 hours.
NA = not available.

12.4 Microbiology

Mechanism of Action

Atazanavir (ATV) is an azapeptide HIV-1 protease inhibitor (PI). The compound selectively inhibits the virus-specific processing of viral Gag and Gag-Pol polyproteins in HIV-1-infected cells, thus preventing formation of mature virions.

Antiviral Activity in Cell Culture

Atazanavir exhibits anti-HIV-1 activity with a mean 50% effective concentration (EC50) in the absence of human serum of 2 to 5 nM against a variety of laboratory and clinical HIV-1 isolates grown in peripheral blood mononuclear cells, macrophages, CEM-SS cells, and MT-2 cells. Atazanavir has activity against HIV-1 Group M subtype viruses A, B, C, D, AE, AG, F, G, and J isolates in cell culture. Atazanavir has variable activity against HIV-2 isolates (1.9-32 nM), with EC50 values above the EC50 values of failure isolates. Two-drug combination antiviral activity studies with atazanavir showed no antagonism in cell culture with PIs (amprenavir, indinavir, lopinavir, nelfinavir, ritonavir, and saquinavir), NNRTIs (delavirdine, efavirenz, and nevirapine), NRTIs (abacavir, didanosine, emtricitabine, lamivudine, stavudine, tenofovir DF, and zidovudine), the HIV-1 fusion inhibitor enfuvirtide, and two compounds used in the treatment of viral hepatitis, adefovir and ribavirin, without enhanced cytotoxicity.

Resistance

In Cell Culture: HIV-1 isolates with a decreased susceptibility to atazanavir have been selected in cell culture and obtained from patients treated with atazanavir or atazanavir with ritonavir. HIV-1 isolates with 93- to 183-fold reduced susceptibility to atazanavir from three different viral strains were selected in cell culture by 5 months. The substitutions in these HIV-1 viruses that contributed to atazanavir resistance include I50L, N88S, I84V, A71V, and M46I. Changes were also observed at the protease cleavage sites following drug selection. Recombinant viruses containing the I50L substitution without other major PI substitutions were growth impaired and displayed increased susceptibility in cell culture to other PIs (amprenavir, indinavir, lopinavir, nelfinavir, ritonavir, and saquinavir). The I50L and I50V substitutions yielded selective resistance to atazanavir and amprenavir, respectively, and did not appear to be cross-resistant.

Clinical Studies of Treatment-Naive Participants: Comparison of Ritonavir-Boosted REYATAZ vs Unboosted REYATAZ: Study AI424-089 compared REYATAZ 300 mg once daily with ritonavir 100 mg vs REYATAZ 400 mg once daily when administered with lamivudine and extended-release stavudine in treatment-naive participants with HIV-1. A summary of the number of virologic failures and virologic failure isolates with atazanavir resistance in each arm is shown in Table 23.

Table 23: Summary of Virologic Failuresa at Week 96 in Study AI424-089: Comparison of Ritonavir Boosted REYATAZ vs Unboosted REYATAZ: Randomized Participants
 | REYATAZ 300 mg with ritonavir 100 mg (n=95) | REYATAZ 400 mg (n=105)
Virologic Failure (≥50 copies/mL) at Week 96 | 15 (16%) | 34 (32%)
Virologic Failure with Genotypes and Phenotypes Data | 5 | 17
Virologic Failure Isolates with atazanavir-resistance at Week 96 | 0/5 (0%)b | 4/17 (24%)b
Virologic Failure Isolates with I50L Emergence at Week 96c | 0/5 (0%)b | 2/17 (12%)b
Virologic Failure Isolates with Lamivudine Resistance at Week 96 | 2/5 (40%)b | 11/17 (65%)b
a Virologic failure includes participants who were never suppressed through Week 96 and on study at Week 96, had virologic rebound or discontinued due to insufficient viral load response.
b Percentage of Virologic Failure Isolates with genotypic and phenotypic data.
c Mixture of I50I/L emerged in 2 other atazanavir 400 mg-treated participants. Neither isolate was phenotypically resistant to atazanavir.

Clinical Studies of Treatment-Naive Participants Receiving REYATAZ 300 mg with Ritonavir 100 mg: In Phase 3 Study AI424-138, an as-treated genotypic and phenotypic analysis was conducted on samples from participants who experienced virologic failure (HIV-1 RNA ≥400 copies/mL) or discontinued before achieving suppression on atazanavir with ritonavir (n=39; 9%) and lopinavir/ritonavir (n=39; 9%) through 96 weeks of treatment. In the atazanavir with ritonavir arm, one of the virologic failure isolates had a 56-fold decrease in atazanavir susceptibility emerge on therapy with the development of PI resistance-associated substitutions L10F, V32I, K43T, M46I, A71I, G73S, I85I/V, and L90M. The NRTI resistance-associated substitution M184V also emerged on treatment in this isolate conferring emtricitabine resistance. Two atazanavir with ritonavir-virologic failure isolates had baseline phenotypic atazanavir resistance and IAS-defined major PI resistance-associated substitutions at baseline. The I50L substitution emerged on study in one of these failure isolates and was associated with a 17-fold decrease in atazanavir susceptibility from baseline and the other failure isolate with baseline atazanavir resistance and PI substitutions (M46M/I and I84I/V) had additional IAS-defined major PI substitutions (V32I, M46I, and I84V) emerge on atazanavir treatment associated with a 3-fold decrease in atazanavir susceptibility from baseline. Five of the treatment failure isolates in the atazanavir with ritonavir arm developed phenotypic emtricitabine resistance with the emergence of either the M184I (n=1) or the M184V (n=4) substitution on therapy and none developed phenotypic tenofovir disoproxil resistance. In the lopinavir/ritonavir arm, one of the virologic failure participant isolates had a 69-fold decrease in lopinavir susceptibility emerge on therapy with the development of PI substitutions L10V, V11I, I54V, G73S, and V82A in addition to baseline PI substitutions L10L/I, V32I, I54I/V, A71I, G73G/S, V82V/A, L89V, and L90M. Six lopinavir/ritonavir virologic failure isolates developed the M184V substitution and phenotypic emtricitabine resistance and two developed phenotypic tenofovir disoproxil resistance.

Clinical Studies of Treatment-Naive Participants Receiving REYATAZ 400 mg without Ritonavir: atazanavir-resistant clinical isolates from treatment-naive participants who experienced virologic failure on REYATAZ 400 mg treatment without ritonavir often developed an I50L substitution (after an average of 50 weeks of atazanavir therapy), often in combination with an A71V substitution, but also developed one or more other PI substitutions (eg, V32I, L33F, G73S, V82A, I85V, or N88S) with or without the I50L substitution. In treatment-naive participants, viral isolates that developed the I50L substitution, without other major PI substitutions, showed phenotypic resistance to atazanavir but retained in cell culture susceptibility to other PIs (amprenavir, indinavir, lopinavir, nelfinavir, ritonavir, and saquinavir); however, there are no clinical data available to demonstrate the effect of the I50L substitution on the efficacy of subsequently administered PIs.

Clinical Studies of Treatment-Experienced Participants: In studies of treatment-experienced participants treated with atazanavir or atazanavir with ritonavir, most atazanavir-resistant isolates from participants who experienced virologic failure developed substitutions that were associated with resistance to multiple PIs and displayed decreased susceptibility to multiple PIs. The most common protease substitutions to develop in the viral isolates of participants who failed treatment with atazanavir 300 mg once daily and ritonavir 100 mg once daily (together with tenofovir DF and an NRTI) included V32I, L33F/V/I, E35D/G, M46I/L, I50L, F53L/V, I54V, A71V/T/I, G73S/T/C, V82A/T/L, I85V, and L89V/Q/M/T. Other substitutions that developed on atazanavir with ritonavir treatment including E34K/A/Q, G48V, I84V, N88S/D/T, and L90M occurred in less than 10% of participant isolates. Generally, if multiple PI resistance substitutions were present in the HIV-1 virus of the participant at baseline, atazanavir resistance developed through substitutions associated with resistance to other PIs and could include the development of the I50L substitution. The I50L substitution has been detected in treatment-experienced participants experiencing virologic failure after long-term treatment. Protease cleavage site changes also emerged on atazanavir treatment, but their presence did not correlate with the level of atazanavir resistance.

Clinical Studies of Pediatric Participants in AI424-397 (PRINCE I) and AI424-451 (PRINCE II): Treatment-emergent atazanavir with ritonavir resistance-associated amino acid substitution M36I in the protease was detected in the virus of one participant among treatment failures in AI424-397. In addition, three known resistance-associated substitutions for other PIs arose in the viruses from one participant each (L19I/R, H69K/R, and I72I/V). Reduced susceptibility to atazanavir, ritonavir, or atazanavir with ritonavir was not seen with these viruses. In AI424-451, atazanavir with ritonavir resistance-associated substitutions G16E, V82A/I/T, I84V, and/or L90M arose in the viruses of two participants. The virus population harboring the M46M/V, V82V/I, I84I/V, and L90L/M substitutions acquired phenotypic resistance to ritonavir (ritonavir phenotypic fold-change of 3.5, with a ritonavir cutoff of 2.5-fold change). However, these substitutions did not result in phenotypic resistance to atazanavir (atazanavir phenotypic fold-change of <1.8, with an atazanavir cutoff of 2.2-fold change). Secondary PI resistance-associated amino acid substitutions also arose in the viruses of one participant each, including V11V/I, D30D/G, E35E/D, K45K/R, L63P/S, and I72I/T. Q61D and Q61E/G emerged in the viruses of two participants who failed treatment with atazanavir with ritonavir. Viruses from nine participants in the two studies developed NRTI resistance-associated substitutions: K65K/R (n=1), M184V (n=7), and T215I (n=1).

Cross-Resistance

Cross-resistance among PIs has been observed. Baseline phenotypic and genotypic analyses of clinical isolates from atazanavir clinical trials of PI-experienced participants showed that isolates cross-resistant to multiple PIs were cross-resistant to atazanavir. Greater than 90% of the isolates with substitutions that included I84V or G48V were resistant to atazanavir. Greater than 60% of isolates containing L90M, G73S/T/C, A71V/T, I54V, M46I/L, or a change at V82 were resistant to atazanavir, and 38% of isolates containing a D30N substitution in addition to other changes were resistant to atazanavir. Isolates resistant to atazanavir were also cross-resistant to other PIs with >90% of the isolates resistant to indinavir, lopinavir, nelfinavir, ritonavir, and saquinavir, and 80% resistant to amprenavir. In treatment-experienced participants, PI-resistant viral isolates that developed the I50L substitution in addition to other PI resistance-associated substitution were also cross-resistant to other PIs.

Baseline Genotype/Phenotype and Virologic Outcome Analyses

Genotypic and/or phenotypic analysis of baseline virus may aid in determining atazanavir susceptibility before initiation of atazanavir with ritonavir therapy. An association between virologic response at 48 weeks and the number and type of primary PI resistance-associated substitutions detected in baseline HIV-1 isolates from antiretroviral-experienced participants receiving atazanavir with ritonavir once daily or lopinavir / ritonavir (fixed-dose product) twice daily in Study AI424-045 is shown in Table 24.

Overall, both the number and type of baseline PI substitutions affected response rates in treatment-experienced participants. In the atazanavir with ritonavir group, participants had lower response rates when 3 or more baseline PI substitutions, including a substitution at position 36, 71, 77, 82, or 90, were present compared to participants with 1–2 PI substitutions, including one of these substitutions.

Table 24: HIV RNA Response by Number and Type of Baseline PI Substitution, Antiretroviral-Experienced Participants in Study AI424-045, As-Treated Analysis
 | Virologic Response = HIV-1 RNA <400 copies/mLb
Number and Type of Baseline PI Substitutionsa | atazanavir with ritonavir (n=110) | lopinavir/ritonavirc (n=113)
3 or more primary PI substitutions includingd:
D30N | 75% (6/8) | 50% (3/6)
M36I/V | 19% (3/16) | 33% (6/18)
M46I/L/T | 24% (4/17) | 23% (5/22)
I54V/L/T/M/A | 31% (5/16) | 31% (5/16)
A71V/T/I/G | 34% (10/29) | 39% (12/31)
G73S/A/C/T | 14% (1/7) | 38% (3/8)
V77I | 47% (7/15) | 44% (7/16)
V82A/F/T/S/I | 29% (6/21) | 27% (7/26)
I84V/A | 11% (1/9) | 33% (2/6)
N88D | 63% (5/8) | 67% (4/6)
L90M | 10% (2/21) | 44% (11/25)
Number of baseline primary PI substitutionsa
All patients, as-treated | 58% (64/110) | 59% (67/113)
0–2 PI substitutions | 75% (50/67) | 75% (50/67)
3–4 PI substitutions | 41% (14/34) | 43% (12/28)
5 or more PI substitutions | 0% (0/9) | 28% (5/18)
a Primary substitutions include any change at D30, V32, M36, M46, I47, G48, I50, I54, A71, G73, V77, V82, I84, N88, and L90.
b Results should be interpreted with caution because the subgroups were small.
c Administered as a fixed-dose product.
d There were insufficient data (n<3) for PI substitutions V32I, I47V, G48V, I50V, and F53L.

The response rates of antiretroviral-experienced participants in Study AI424-045 were analyzed by baseline phenotype (shift in susceptibility in cell culture relative to reference, Table 25). The analyses are based on a select population with 62% of participants receiving an NNRTI-based regimen before study entry compared to 35% receiving a PI-based regimen. Additional data are needed to determine clinically relevant break points for REYATAZ.

Table 25: Baseline Phenotype by Outcome, Antiretroviral-Experienced Participants in Study AI424-045, As-Treated Analysis
 | Virologic Response = HIV-1 RNA <400 copies/mLb
Baseline Phenotypea | atazanavir with ritonavir (n=111) | lopinavir/ritonavirc (n=111)
0–2 | 71% (55/78) | 70% (56/80)
>2–5 | 53% (8/15) | 44% (4/9)
>5–10 | 13% (1/8) | 33% (3/9)
>10 | 10% (1/10) | 23% (3/13)
a Fold change susceptibility in cell culture relative to the wild-type reference.
b Results should be interpreted with caution because the subgroups were small.
c Administered as a fixed-dose product.

13 NONCLINICAL TOXICOLOGY

13.1 Carcinogenesis, Mutagenesis, Impairment of Fertility

Carcinogenesis

Long-term carcinogenicity studies in mice and rats were carried out with atazanavir for two years. In the mouse study, drug-related increases in hepatocellular adenomas were found in females at 360 mg/kg/day. The systemic drug exposure (AUC) at the NOAEL (no observable adverse effect level) in females, (120 mg/kg/day) was 2.8 times and in males (80 mg/kg/day) was 2.9 times higher than those in humans at the clinical dose (300 mg/day atazanavir boosted with 100 mg/day ritonavir, non-pregnant patients). In the rat study, no drug-related increases in tumor incidence were observed at doses up to 1200 mg/kg/day, for which AUCs were 1.1 (males) or 3.9 (females) times those measured in humans at the clinical dose.

Mutagenesis

Atazanavir tested positive in an in vitro clastogenicity test using primary human lymphocytes, in the absence and presence of metabolic activation. Atazanavir tested negative in the in vitro Ames reverse-mutation assay, in vivo micronucleus and DNA repair tests in rats, and in vivo DNA damage test in rat duodenum (comet assay).

Impairment of Fertility

At the systemic drug exposure levels (AUC) 0.9 (in male rats) or 2.3 (in female rats) times that of the human clinical dose, (300 mg/day atazanavir boosted with 100 mg/day ritonavir) significant effects on mating, fertility, or early embryonic development were not observed.

14 CLINICAL STUDIES

14.1 Adult Participants without Prior Antiretroviral Therapy

Study AI424-138: a 96-week study comparing the antiviral efficacy and safety of either REYATAZ or lopinavir/ritonavir, each in combination with fixed-dose tenofovir DF-emtricitabine in treatment-naive participants with HIV-1 infection. Study AI424-138 (NCT00272779) was a 96-week, open-label, randomized, multicenter study, comparing REYATAZ (300 mg once daily) with ritonavir (100 mg once daily) to lopinavir/ritonavir (400/100 mg twice daily as fixed-dose product), each in combination with the fixed-dose product, tenofovir DF/emtricitabine (300/200 mg once daily), in 878 antiretroviral treatment-naive participants. Participants had a mean age of 36 years (range: 19-72), 49% were Caucasian, 18% Black, 9% Asian, 23% Hispanic/Mestizo/mixed race, and 68% were male. The median baseline plasma CD4+ cell count was 204 cells/mm3 (range: 2 to 810 cells/mm3) and the mean baseline plasma HIV-1 RNA level was 4.94 log10 copies/mL (range: 2.60 to 5.88 log10 copies/mL). Treatment response and outcomes through Week 96 are presented in Table 26.

Table 26: Outcomes of Treatment Through Week 96 in Treatment-Naive Adults (Study AI424-138)
 | REYATAZ 300 mg with ritonavir 100 mg (once daily) and tenofovir DF/emtricitabine (once daily)a (n=441) | lopinavir/ritonavirb 400 mg/100 mg (twice daily) with tenofovir DF/emtricitabine (once daily)a (n=437)
Outcome | 96 Weeks | 96 Weeks
Responderc,d,e | 75% | 68%
Virologic failuref | 17% | 19%
Rebound | 8% | 10%
Never suppressed through Week 96 | 9% | 9%
Death | 1% | 1%
Discontinued due to adverse event | 3% | 5%
Discontinued for other reasonsg | 4% | 7%
a As a fixed-dose product: 300 mg tenofovir DF/200 mg emtricitabine once daily.
b As a fixed-dose product: 400 mg lopinavir/100 mg ritonavir (twice daily).
c Participants achieved HIV-1 RNA <50 copies/mL at Week 96. Roche Amplicor®, v1.5 ultra-sensitive assay.
d Pre-specified ITT analysis at Week 48 using as-randomized cohort: atazanavir with ritonavir 78% and lopinavir/ritonavir 76% (difference estimate: 1.7% [95% confidence interval: −3.8%, 7.1%]).
e Pre-specified ITT analysis at Week 96 using as-randomized cohort: atazanavir with ritonavir 74% and lopinavir/ritonavir 68% (difference estimate: 6.1% [95% confidence interval: 0.3%, 12.0%]).
f Includes viral rebound and failure to achieve confirmed HIV-1 RNA <50 copies/mL through Week 96.
g Includes lost to follow-up, participant’s withdrawal, noncompliance, protocol violation, and other reasons.

Through 96 weeks of therapy, the proportion of responders among participants with high viral loads (ie, baseline HIV-1 RNA ≥100,000 copies/mL) was comparable for the REYATAZ with ritonavir (165 of 223 participants, 74%) and lopinavir/ritonavir (148 of 222 participants, 67%) arms. At 96 weeks, the median increase from baseline in CD4+ cell count was 261 cells/mm^3 for the REYATAZ with ritonavir arm and 273 cells/mm^3 for the lopinavir/ritonavir arm.

Study AI424-034: REYATAZ once daily compared to efavirenz once daily, each in combination with fixed-dose lamivudine/zidovudine twice daily. Study AI424-034 (NCT00013897) was a randomized, double-blind, multicenter trial comparing REYATAZ (400 mg once daily) to efavirenz (600 mg once daily), each in combination with the fixed-dose product of lamivudine /zidovudine (150 mg/300 mg) given twice daily, in 810 antiretroviral treatment-naive participants. Participants had a mean age of 34 years (range: 18 to 73), 36% were Hispanic, 33% were Caucasian, and 65% were male. The mean baseline CD4+ cell count was 321 cells/mm^3 (range: 64 to 1424 cells/mm^3) and the mean baseline plasma HIV-1 RNA level was 4.8 log10 copies/mL (range: 2.2 to 5.9 log10 copies/mL). Treatment response and outcomes through Week 48 are presented in Table 27.

Table 27: Outcomes of Randomized Treatment Through Week 48 in Treatment-Naive Adults (Study AI424-034)
Outcome | REYATAZ 400 mg once daily and lamivudine/zidovudined (n=405) | efavirenz 600 mg once daily and lamivudine/zidovudined (n=405)
Respondera | 67% (32%) | 62% (37%)
Virologic failureb | 20% | 21%
Rebound | 17% | 16%
Never suppressed through Week 48 | 3% | 5%
Death | – | <1%
Discontinued due to adverse event | 5% | 7%
Discontinued for other reasonsc | 8% | 10%
a Participants achieved and maintained confirmed HIV-1 RNA <400 copies/mL (<50 copies/mL) through Week 48. Roche Amplicor® HIV-1 Monitor™ Assay, test version 1.0 or 1.5 as geographically appropriate.
b Includes viral rebound and failure to achieve confirmed HIV-1 RNA <400 copies/mL through Week 48.
c Includes lost to follow-up, participant’s withdrawal, noncompliance, protocol violation, and other reasons.
d As a fixed-dose product: 150 mg lamivudine/300 mg zidovudine twice daily.

Through 48 weeks of therapy, the proportion of responders among participants with high viral loads (ie, baseline HIV-1 RNA ≥100,000 copies/mL) was comparable for the REYATAZ and efavirenz arms. The mean increase from baseline in CD4+ cell count was 176 cells/mm^3 for the REYATAZ arm and 160 cells/mm^3 for the efavirenz arm.

Study AI424-008: REYATAZ 400 mg once daily compared to REYATAZ 600 mg once daily, and compared to nelfinavir 1250 mg twice daily, each in combination with stavudine and lamivudine twice daily. Study AI424-008 (NCT identifier not available) was a 48-week, randomized, multicenter trial, blinded to dose of REYATAZ, comparing REYATAZ at two dose levels (400 mg and 600 mg once daily) to nelfinavir (1250 mg twice daily), each in combination with stavudine (40 mg) and lamivudine (150 mg) given twice daily, in 467 antiretroviral treatment-naive participants. Participants had a mean age of 35 years (range: 18 to 69), 55% were Caucasian, and 63% were male. The mean baseline CD4+ cell count was 295 cells/mm^3 (range: 4 to 1003 cells/mm^3) and the mean baseline plasma HIV-1 RNA level was 4.7 log10 copies/mL (range: 1.8 to 5.9 log10 copies/mL). Treatment response and outcomes through Week 48 are presented in Table 28.

Table 28: Outcomes of Randomized Treatment Through Week 48 in Treatment-Naive Adults (Study AI424-008)
Outcome | REYATAZ 400 mg once daily with lamivudine and stavudine (n=181) | nelfinavir 1250 mg twice daily with lamivudine and stavudine (n=91)
Respondera | 67% (33%) | 59% (38%)
Virologic failureb | 24% | 27%
Rebound | 14% | 14%
Never suppressed through Week 48 | 10% | 13%
Death | <1% | –
Discontinued due to adverse event | 1% | 3%
Discontinued for other reasonsc | 7% | 10%
a Participants achieved and maintained confirmed HIV-1 RNA <400 copies/mL (<50 copies/mL) through Week 48. Roche Amplicor® HIV-1 Monitor™ Assay, test version 1.0 or 1.5 as geographically appropriate.
b Includes viral rebound and failure to achieve confirmed HIV-1 RNA <400 copies/mL through Week 48.
c Includes lost to follow-up, participant’s withdrawal, noncompliance, protocol violation, and other reasons.

Through 48 weeks of therapy, the mean increase from baseline in CD4+ cell count was 234 cells/mm^3 for the REYATAZ 400-mg arm and 211 cells/mm^3 for the nelfinavir arm.

14.2 Adult Participants with Prior Antiretroviral Therapy

Study AI424-045: REYATAZ once daily with ritonavir once daily compared to REYATAZ once daily and saquinavir (soft gelatin capsules) once daily, and compared to lopinavir/ritonavir twice daily, each in combination with tenofovir DF and one NRTI. Study AI424-045 (NCT00035932): was a randomized, multicenter trial comparing REYATAZ (300 mg once daily) with ritonavir (100 mg once daily) to REYATAZ (400 mg once daily) with saquinavir soft gelatin capsules (1200 mg once daily), and to lopinavir/ritonavir (400/100 mg twice daily as fixed-dose product), each in combination with tenofovir DF and one NRTI, in 347 (of 358 randomized) participants who experienced virologic failure on highly active antiretroviral therapy regimens containing PIs, NNRTIs, and NRTIs. The mean time of prior exposure to antiretrovirals was 139 weeks for PIs, 85 weeks for NNRTIs, and 283 weeks for NRTIs. The mean age was 41 years (range: 24 to 74); 60% were Caucasian, and 78% were male. The mean baseline CD4+ cell count was 338 cells/mm^3 (range: 14 to 1543 cells/mm^3) and the mean baseline plasma HIV-1 RNA level was 4.4 log10 copies/mL (range: 2.6 to 5.88 log10 copies/mL).

Treatment outcomes through Week 48 for the REYATAZ with ritonavir and lopinavir/ritonavir treatment arms are presented in Table 29. REYATAZ with ritonavir and lopinavir/ritonavir were similar for the primary efficacy outcome measure of time-averaged difference in change from baseline in HIV-1 RNA level. Study AI424-045 was not large enough to reach a definitive conclusion that REYATAZ with ritonavir and lopinavir/ritonavir are equivalent on the secondary efficacy outcome measure of proportions below the HIV-1 RNA lower limit of quantification [see Microbiology, Tables 24 and 25 (12.4)].

Table 29: Outcomes of Treatment Through Week 48 in Study AI424-045 (Participants with Prior Antiretroviral Experience)
Outcome | REYATAZ 300 mg with ritonavir 100 mg once daily and tenofovir DF and 1 NRTI (n=119) | lopinavir/ritonavir (400/100 mg) twice daily and tenofovir DF and 1 NRTI; (n=118) | Differencea (REYATAZ-lopinavir/ritonavir)b (CI)
HIV-1 RNA Change from Baseline (log10 copies/mL)c | −1.58 | −1.70 | +0.12c (−0.17, 0.41)
CD4+ Change from Baseline (cells/mm^3)e | 116 | 123 | −7 (−67, 52)
Percent of Participants Respondinge
HIV-1 RNA <400 copies/mLc | 55% | 57% | −2.2% (−14.8%, 10.5%)
HIV-1 RNA <50 copies/mLc | 38% | 45% | −7.1% (−19.6%, 5.4%)
a Time-averaged difference through Week 48 for HIV-1 RNA; Week 48 difference in HIV-1 RNA percentages and CD4+ mean changes, REYATAZ with ritonavir vs lopinavir/ritonavir; CI = 97.5% confidence interval for change in HIV-1 RNA; 95% confidence interval otherwise.
b Administered as a fixed-dose product.
c Roche Amplicor® HIV-1 Monitor™ Assay, test version 1.5.
d Protocol-defined primary efficacy outcome measure.
e Based on participants with baseline and Week 48 CD4+ cell count measurements (REYATAZ with ritonavir, n=85; lopinavir/ritonavir, n=93).
f Participants achieved and maintained confirmed HIV-1 RNA <400 copies/mL (<50 copies/mL) through Week 48.

No participants in the REYATAZ with ritonavir treatment arm and three participants in the lopinavir/ritonavir treatment arm experienced a new-onset CDC Category C event during the study.

In Study AI424-045, the mean change from baseline in plasma HIV-1 RNA for REYATAZ 400 mg with saquinavir (n=115) was −1.55 log10 copies/mL, and the time-averaged difference in change in HIV-1 RNA levels versus lopinavir/ritonavir was 0.33. The corresponding mean increase in CD4+ cell count was 72 cells/mm^3. Through 48 weeks of treatment, the proportion of participants in this treatment arm with plasma HIV-1 RNA <400 (<50) copies/mL was 38% (26%). In this study, coadministration of REYATAZ and saquinavir did not provide adequate efficacy [see Drug Interactions (7)].

Study AI424-045 also compared changes from baseline in lipid values. [See Adverse Reactions (6.1).]

Study AI424-043 (NCT00028301): Study AI424-043 was a randomized, open-label, multicenter trial comparing REYATAZ (400 mg once daily) to lopinavir/ritonavir (400/100 mg twice daily as fixed-dose product), each in combination with two NRTIs, in 300 participants who experienced virologic failure to only one prior PI-containing regimen. Through 48 weeks, the proportion of participants with plasma HIV-1 RNA <400 (<50) copies/mL was 49% (35%) for participants randomized to REYATAZ (n=144) and 69% (53%) for participants randomized to lopinavir/ritonavir (n=146). The mean change from baseline was −1.59 log10 copies/mL in the REYATAZ treatment arm and −2.02 log10 copies/mL in the lopinavir/ritonavir arm. Based on the results of this study, REYATAZ without ritonavir was inferior to lopinavir/ritonavir in PI-experienced participants with prior virologic failure and is not recommended for such patients.

14.3 Pediatric Participants

Pediatric Trials with REYATAZ Capsules

Study AI424-040; PACTG 1020A (NCT00006604): Assessment of the pharmacokinetics, safety, tolerability, and virologic response of REYATAZ capsules was based on data from this open-label, multicenter clinical trial which included participants from 6 years to 21 years of age. In this study, 105 participants (43 antiretroviral-naive and 62 antiretroviral-experienced) received once daily REYATAZ capsule formulation, with or without ritonavir, in combination with two NRTIs.

One-hundred five (105) participants (6 to less than 18 years of age) treated with the REYATAZ capsule formulation, with or without ritonavir, were evaluated. Using an intent-to-treat (ITT) analysis, the overall proportions of antiretroviral-naive and -experienced participants with HIV-1 RNA <400 copies/mL at Week 96 were 51% (22/43) and 34% (21/62), respectively. The overall proportions of antiretroviral-naive and -experienced participants with HIV-1 RNA <50 copies/mL at Week 96 were 47% (20/43) and 24% (15/62), respectively. The median increase from baseline in absolute CD4 count at 96 weeks of therapy was 335 cells/mm^3 in antiretroviral-naive participants and 220 cells/mm^3 in antiretroviral-experienced participants.

Pediatric Trials with REYATAZ Oral Powder

Assessment of the pharmacokinetics, safety, tolerability, and virologic response of REYATAZ oral powder was based on data from two open-label, multicenter clinical trials.

- AI424-397 (PRINCE I; NCT01099579): In pediatric participants from 3 months to less than 6 years of age
- AI424-451 (PRINCE II; NCT01335698): In pediatric participants from 3 months to less than 11 years of age

In these studies, 155 participants (59 antiretroviral-naive and 96 antiretroviral-experienced) received once daily REYATAZ oral powder with ritonavir, in combination with two NRTIs.

For inclusion in both trials, treatment-naive participants had to have genotypic sensitivity to REYATAZ and two NRTIs, and treatment-experienced participants had to have documented genotypic and phenotypic sensitivity at screening to REYATAZ and at least 2 NRTIs. Participants exposed only to antiretrovirals in utero or intrapartum were considered treatment-naive. Participants who received REYATAZ or REYATAZ with ritonavir at any time prior to study enrollment or who had a history of treatment failure on two or more protease inhibitors were excluded from the trials.

One hundred thirty-four (134) participants from both studies weighing 5 kg to less than 35 kg treated with REYATAZ oral powder with ritonavir were evaluated. Participants 5 kg to less than 10 kg received either 150 mg or 200 mg REYATAZ and 80 mg ritonavir oral solution; participants 10 kg to less than 15 kg received 200 mg REYATAZ and 80 mg ritonavir oral solution; participants 15 kg to less than 25 kg received 250 mg REYATAZ and 80 mg ritonavir oral solution; and participants 25 kg to less than 35 kg received 300 mg REYATAZ and 100 mg ritonavir.

Using a modified ITT analysis, the overall proportions of antiretroviral-naive and antiretroviral-experienced participants with HIV-1 RNA <400 copies/mL at Week 48 were 79% (41/52) and 62% (51/82), respectively in participants who received REYATAZ oral powder with ritonavir. The overall proportions of antiretroviral-naive and antiretroviral-experienced participants with HIV-1 RNA <50 copies/mL at Week 48 were 54% (28/52) and 50% (41/82), respectively, in participants who received REYATAZ oral powder with ritonavir. The median increase from baseline in absolute CD4 count (percent) at 48 weeks of therapy (last observation carried forward) was 215 cells/mm^3 (6%) in antiretroviral-naive participants and 133 cells/mm^3 (4%) in antiretroviral-experienced participants who received REYATAZ oral powder with ritonavir.

16 HOW SUPPLIED/STORAGE AND HANDLING

REYATAZ Capsules

REYATAZ® (atazanavir) capsules are available in the following strengths and configurations of plastic bottles with child-resistant closures.

Product Strength* | Capsule Shell Color (cap/body) | Markings on Capsule (ink color) |  | Capsules per Bottle | NDC Number
Product Strength* | Capsule Shell Color (cap/body) | cap | body | Capsules per Bottle | NDC Number
200 mg | blue/blue | BMS 200 mg (white) | 3631 (white) | 60 | 0003-3631-12
300 mg | red/blue | BMS 300 mg (white) | 3622 (white) | 30 | 0003-3622-12
* 200 mg atazanavir equivalent to 227.8 mg atazanavir sulfate.
300 mg atazanavir equivalent to 341.69 mg atazanavir sulfate.

Keep capsules in a tightly closed container.

Store REYATAZ capsules at 25°C (77°F); excursions permitted to 15°C to 30°C (59°F to 86°F) [see USP Controlled Room Temperature].

REYATAZ oral powder is an orange-vanilla flavored powder, packed in child-resistant packets. Each packet contains 50 mg of atazanavir equivalent to 56.9 mg of atazanavir sulfate in 1.5 g of powder. REYATAZ oral powder is supplied in cartons (NDC 0003-3638-10) of 30 packets each. [See Dosage and Administration (2.5)].

Store REYATAZ oral powder at a temperature of 68°F to 86°F (20°C to 30°C). Store REYATAZ oral powder in the original packet. Do not open until ready to use. After REYATAZ oral powder is mixed with food or liquid, it may be kept at a temperature 68°F to 86°F (20°C to 30°C) for up to 1 hour. Take REYATAZ oral powder within 1 hour after mixing with food or liquid.

17 PATIENT COUNSELING INFORMATION

Advise the patient to read the FDA-approved patient labeling (Patient Information and Instructions for Use).

REYATAZ is not a cure for HIV-1 infection. Advise patients to remain under the care of a healthcare provider while using REYATAZ.

Cardiac Conduction Abnormalities

Inform patients that atazanavir may produce changes in the electrocardiogram (eg, PR prolongation). Tell patients to consult their healthcare provider if they are experiencing symptoms such as dizziness or lightheadedness [see Warnings and Precautions (5.1)].

Severe Skin Reaction

Inform patients that there have been reports of severe skin reactions (eg, Stevens-Johnson syndrome, erythema multiforme, and toxic skin eruptions) with REYATAZ use. Advise patients that if signs or symptoms of severe skin reactions or hypersensitivity reactions develop, they must discontinue REYATAZ and seek medical evaluation immediately [see Warnings and Precautions (5.2) and Adverse Reactions (6.1)].

Hyperbilirubinemia

Inform patients that asymptomatic elevations in indirect bilirubin have occurred in patients receiving REYATAZ. This may be accompanied by yellowing of the skin or whites of the eyes and alternative antiretroviral therapy may be considered if the patient has cosmetic concerns [see Warnings and Precautions (5.8)].

Patients with Phenylketonuria

Advise caregivers of patients with phenylketonuria that REYATAZ oral powder contains phenylalanine [see Warnings and Precautions (5.3)].

Chronic Kidney Disease

Inform patients that treatment with REYATAZ may lead to the development of chronic kidney disease, and to maintain adequate hydration while taking REYATAZ [see Warnings and Precautions (5.5)].

Nephrolithiasis and Cholelithiasis

Inform patients that kidney stones and/or gallstones have been reported with REYATAZ use. Some patients with kidney stones and/or gallstones required hospitalization for additional management, and some had complications. Discontinuation of REYATAZ may be necessary as part of the medical management of these adverse events [see Warnings and Precautions (5.6)].

Drug Interactions

REYATAZ may lead to significant interaction with some drugs; therefore, advise patients to report the use of any other prescription, nonprescription medication, or herbal products, particularly St. John’s wort, to their healthcare provider prior to use [see Contraindications (4), Warnings and Precautions (5.7)].

Immune Reconstitution Syndrome

Advise patients to inform their healthcare provider immediately of any symptoms of infection, as in some patients with advanced HIV-1, signs and symptoms of inflammation from previous infections may occur soon after anti-HIV-1 treatment is started [see Warnings and Precautions (5.10)].

Fat Redistribution

Inform patients that redistribution or accumulation of body fat may occur in patients receiving antiretroviral therapy including protease inhibitors and that the cause and long-term health effects of these conditions are not known at this time [see Warnings and Precautions (5.11)].

Dosing Instructions

Advise patients to take REYATAZ with food every day and take other concomitant antiretroviral therapy as prescribed. REYATAZ must always be used in combination with other antiretroviral drugs. Advise patients that they should not alter the dose or discontinue therapy without consulting with their healthcare provider. Tell patients if a dose of REYATAZ is missed, they should take the dose as soon as possible and then return to their normal schedule; however, if a dose is skipped the patient should not double the next dose.

Pregnancy

Inform pregnant patients that there is a pregnancy exposure registry that monitors pregnancy outcomes in pregnant patients exposed to REYATAZ during pregnancy. Healthcare providers are encouraged to register patients by calling the Antiretroviral Pregnancy Registry [see Use in Specific Populations (8.1)].

Lactation

Instruct patients with HIV-1 that the potential risks of breastfeeding include: (1) HIV-1 transmission to infants without HIV-1, (2) developing viral resistance in infants with HIV-1, and (3) adverse reactions in a breastfed infant similar to those seen in adults [see Use in Specific Populations (8.2)].

Patient Package Insert

PATIENT INFORMATION

REYATAZ® (RAY-ah-taz)
(atazanavir)
capsules

REYATAZ® (RAY-ah-taz)
(atazanavir)
oral powder

Important: Ask your healthcare provider or pharmacist about medicines that should not be taken with REYATAZ. For more information, see “Do not take REYATAZ if you” and “Before taking REYATAZ”.

What is REYATAZ?

REYATAZ is a prescription medicine that is used to treat human immunodeficiency virus-1 (HIV-1) infection, in combination with other HIV-1 medicines in adults and children 3 months of age and older and who weigh at least 11 pounds (5 kg).

HIV-1 is the virus that causes AIDS (Acquired Immunodeficiency Syndrome).

REYATAZ should not be used in children younger than 3 months of age.

Do not take REYATAZ if you:

- are allergic to atazanavir or any of the ingredients in REYATAZ. See the end of this leaflet for a complete list of ingredients in REYATAZ.
- are taking any of the following medicines. Taking REYATAZ with these medicines may affect how REYATAZ works. REYATAZ may cause serious or life-threatening side effects, or death when used with these medicines:

- alfuzosin
- amiodarone (when REYATAZ is used with ritonavir)
- apalutamide
- carbamazepine
- cisapride
- elbasvir and grazoprevir
- encorafenib
- ergot medicines including:
  - dihydroergotamine
  - ergonovine
  - ergonovine ergotamine
  - methylergonovine
- glecaprevir and pibrentasvir
- indinavir
- irinotecan
- ivosidenib

- lurasidone (when REYATAZ is used with ritonavir)
- lomitapide
- lovastatin
- midazolam, when taken by mouth for sedation
- nevirapine
- phenobarbital
- phenytoin
- pimozide
- quinidine (when REYATAZ is used with ritonavir)
- rifampin
- sildenafil, when used for the treatment of pulmonary arterial hypertension
- simvastatin
- St. John’s wort
- triazolam

Before taking REYATAZ, tell your healthcare provider about all of your medical conditions, including if you:

- have heart problems
- have liver problems, including hepatitis B or C virus
- have phenylketonuria (PKU). The artificial sweetener aspartame in REYATAZ oral powder contains phenylalanine, which can be harmful to people with PKU.
- have kidney problems
- are receiving dialysis treatment
- have diabetes
- have hemophilia
- are pregnant or plan to become pregnant.
  - REYATAZ must be taken with ritonavir during pregnancy.
  - Hormonal forms of birth control, such as injections, vaginal rings or implants, contraceptive patch, and some birth control pills may not work during treatment with REYATAZ. Talk to your healthcare provider about forms of birth control that may be used during treatment with REYATAZ.
  - Pregnancy Exposure Registry. There is a pregnancy exposure registry for people who take REYATAZ during pregnancy. The purpose of this registry is to collect information about the health of you and your baby. Talk to your healthcare provider about how you can take part in this registry.
  - After your baby is born, tell your healthcare provider if your baby’s skin or the white part of their eyes turns yellow.
- are breastfeeding or plan to breastfeed. REYATAZ can pass into your breast milk.
  - Talk to your healthcare provider about the following risks of breastfeeding during treatment with REYATAZ:
- The HIV-1 virus may pass to your baby if your baby does not have the HIV-1 virus.
- The HIV-1 virus may become harder to treat if your baby has the HIV-1 virus.
- Your baby may get side effects from REYATAZ.

Tell your healthcare provider about all the medicines you take, including prescription and over-the-counter medicines, vitamins, and herbal supplements.

Some medicines interact with REYATAZ. Keep a list of your medicines to show your healthcare provider and pharmacist.

- You can ask your healthcare provider or pharmacist for a list of medicines that interact with REYATAZ.
- Do not start taking a new medicine without telling your healthcare provider. Your healthcare provider can tell you if it is safe to take REYATAZ with other medicines.

How should I take REYATAZ?

- Take REYATAZ exactly as your healthcare provider tells you to.
- Do not change your dose or stop taking REYATAZ unless your healthcare provider tells you to.
- Stay under the care of your healthcare provider during treatment with REYATAZ.
- REYATAZ must be used with other HIV-1 medicines.
- Take REYATAZ 1 time each day.
- REYATAZ comes as capsules and oral powder.
- Take REYATAZ capsules and oral powder with food.
- Swallow the capsules whole. Do not open the capsules.
- REYATAZ oral powder must be mixed with food or liquid. Your child’s healthcare provider will prescribe the right dose of REYATAZ based on your child’s weight. See the detailed “Instructions for Use” that comes with REYATAZ oral powder for information about the correct way to mix and give a dose of REYATAZ oral powder to your child.
- REYATAZ oral powder must be taken with ritonavir.
- If you miss a dose of REYATAZ, take it as soon as you remember. Then take the next dose at your regular time. Do not take 2 doses at the same time.
- If you take too much REYATAZ, call your healthcare provider or go to the nearest hospital emergency room right away.

When your supply of REYATAZ starts to run low, get more from your healthcare provider or pharmacy. It is important not to run out of REYATAZ. The amount of HIV-1 in your blood may increase if the medicine is stopped for even a short time. The virus may become resistant to REYATAZ and harder to treat.

What are the possible side effects of REYATAZ?

REYATAZ can cause serious side effects, including:

- A change in the way your heart beats (heart rhythm change). Tell your healthcare provider right away if you get dizzy or lightheaded. These could be symptoms of a heart problem.
- Skin rash. Skin rash is common with REYATAZ but can sometimes be severe. Severe rash may develop with other symptoms which could be serious. If you develop a severe rash or a rash with any of the following symptoms, stop taking REYATAZ and call your healthcare provider or go to the nearest hospital emergency room right away:

- general feeling of discomfort or “flu-like” symptoms
- fever
- muscle or joint aches
- red or inflamed eyes, like “pink eye” (conjunctivitis)

- blisters
- mouth sores
- swelling of your face
- painful, warm, or red lump under your skin

- Liver problems. If you have liver problems, including hepatitis B or C virus, your liver problems may get worse when you take REYATAZ. Your healthcare provider will do blood tests to check your liver before you start REYATAZ and during treatment. Tell your healthcare provider right away if you get any of the following symptoms:

- dark “tea-colored” urine
- your skin or the white part of your eyes turns yellow
- light colored stools

- nausea
- itching
- stomach-area pain

- Chronic kidney disease. REYATAZ may affect how well your kidneys work. Your healthcare provider will do blood and urine tests to check your kidneys before you start REYATAZ and during treatment. Drink plenty of fluids during treatment with REYATAZ.
- Kidney stones have happened in some people who take REYATAZ, and sometimes may lead to hospitalization. Tell your healthcare provider right away if you get symptoms of kidney stones which may include pain in your low back or low stomach area, blood in your urine, or pain when you urinate.
- Gallbladder stones have happened in some people who take REYATAZ, and sometimes may lead to hospitalization. Tell your healthcare provider right away if you get symptoms of a gallbladder problem which may include:

- pain in the right or middle upper stomach area
- fever

- nausea and vomiting
- your skin or the white part of your eyes turns yellow

- Yellowing of your skin or the white part of your eyes is common with REYATAZ but may be a symptom of a serious problem. These symptoms may be due to increases in bilirubin levels in your blood (bilirubin is made by the liver). Tell your healthcare provider right away if your skin or the white part of your eyes turns yellow.
- New or worsening diabetes and high blood sugar (hyperglycemia) have happened in some people who take protease inhibitor medicines like REYATAZ. Some people have had to start taking medicine to treat diabetes or have changes to their dose of their diabetes medicine. Tell your healthcare provider if you notice an increase in thirst or if you start urinating more often while taking REYATAZ.
- Changes in your immune system (Immune Reconstitution Syndrome) can happen when you start taking HIV-1 medicines. Your immune system may get stronger and begin to fight infections that have been hidden in your body for a long time. Tell your healthcare provider if you start having new symptoms after starting REYATAZ.
- Changes in body fat can happen in people taking HIV-1 medicines. These changes may include increased amount of fat in the upper back and neck (“buffalo hump”), breast, and around the main part of your body (trunk). Loss of fat from the legs, arms, and face may also happen. The exact cause and long-term health effects of these conditions are not known.
- Increased bleeding problems in people with hemophilia have happened when taking protease inhibitors like REYATAZ.

The most common side effects of REYATAZ include:

- nausea
- headache
- stomach-area pain
- vomiting
- trouble sleeping
- numbness, tingling, or burning of hands or feet

- dizziness
- muscle pain
- diarrhea
- depression
- fever

Tell your healthcare provider if you have any side effect that bothers you or that does not go away.

These are not all the possible side effects of REYATAZ. For more information, ask your healthcare provider or pharmacist.

Call your doctor for medical advice about side effects. You may report side effects to FDA at 1-800-FDA-1088.

How should I store REYATAZ?

REYATAZ capsules:

- Store REYATAZ capsules at room temperature, between 68°F to 77°F (20°C to 25°C).
- Keep capsules in a tightly closed container.
- The REYATAZ bottle comes with a child-resistant closure.

REYATAZ oral powder:

- Store REYATAZ oral powder at a temperature of 68°F to 86°F (20°C to 30°C).
- Store REYATAZ oral powder in the original packet. Do not open until ready to use.
- After REYATAZ oral powder is mixed with food or liquid it may be kept at a temperature of 68°F to 86°F (20°C to 30°C) for up to 1 hour. Take REYATAZ oral powder within 1 hour after mixing with food or liquid.

Keep REYATAZ and all medicines out of the reach of children.

General information about the safe and effective use of REYATAZ

Medicines are sometimes prescribed for purposes other than those listed in a Patient Information leaflet. Do not use REYATAZ for a condition for which it was not prescribed. Do not give REYATAZ to other people, even if they have the o same symptoms that you have. It may harm them. If you would like more information, talk with your healthcare provider. You can ask your pharmacist or healthcare provider for information about REYATAZ that is written for health professionals.

For more information, go to www.reyataz.com or call 1-800-321-1335.

What are the ingredients in REYATAZ?

Active ingredient: atazanavir sulfate

Inactive ingredients:

REYATAZ capsules: crospovidone, lactose monohydrate, and magnesium stearate. The capsule shells contain gelatin, FD&C Blue No. 2, titanium dioxide, black iron oxide, red iron oxide, and yellow iron oxide. The capsules are printed with ink containing shellac, titanium dioxide, FD&C Blue No. 2, isopropyl alcohol, ammonium hydroxide, propylene glycol, n-butyl alcohol, simethicone, and dehydrated alcohol.

REYATAZ oral powder: aspartame, sucrose, and orange-vanilla flavor.

Distributed by:

Bristol-Myers Squibb Company, Princeton, NJ 08543 USA.

REYATAZ® is a registered trademark of Bristol-Myers Squibb Company. Other brands listed are the trademarks of their respective owners and are not trademarks of Bristol-Myers Squibb Company.

This Patient Information has been approved by the U.S. Food and Drug Administration.

Revised: December 2024

[print code]

Instructions for Use

REYATAZ® (RAY-ah-taz)
(atazanavir)
oral powder

Read this Instructions for Use before you prepare your child’s first dose of REYATAZ oral powder, each time you get a refill, and as needed. There may be new information. This information does not take the place of talking to your child’s healthcare provider about their medical condition or treatment. Ask your child’s healthcare provider or pharmacist if you have questions about how to mix or give a dose of REYATAZ oral powder.

Important information:

- For more information about REYATAZ oral powder, see the Patient Information leaflet.
- REYATAZ oral powder must be mixed with food or liquid. If REYATAZ oral powder is mixed with water, your child must eat food right after taking REYATAZ oral powder.
- REYATAZ oral powder must be taken with ritonavir.
- Talk with your child’s healthcare provider to help decide the best schedule for giving your child REYATAZ oral powder.

Instructions for mixing REYATAZ oral powder:

REYATAZ oral powder should be mixed with food such as applesauce or yogurt, instead of a liquid (milk, infant formula, or water) in young children and infants who can take food.

- Infants less than 6 months old and who cannot eat solid food or drink from a cup should be given REYATAZ oral powder mixed with infant formula using an oral dosing syringe.
- REYATAZ oral powder that is mixed in infant formula or liquid should not be given using a baby bottle.

When preparing REYATAZ oral powder with either food or liquid, choose a clean, flat work surface. Place a clean paper towel on the work surface. Place the supplies you will need on the paper towel.

Wash and dry your hands before and after preparing REYATAZ oral powder.

Preparing a dose of REYATAZ oral powder mixed with food:

Before you prepare a dose of REYATAZ oral powder mixed with food, gather the following supplies:

- paper towel
- tablespoon
- small clean container (such as a small cup or bowl)
- a food such as applesauce or yogurt
- the correct number of packets of REYATAZ oral powder needed for the prescribed dose
- a clean pair of scissors

Step 1. Place at least 1 tablespoon of a food such as applesauce or yogurt in the small container (see Figure A).

Figure A

Step 2. Tap the packet of REYATAZ oral powder to settle the contents to the bottom of the packet (see Figure B).

Figure B

Step 3. Using a clean pair of scissors, cut open the packet on the dotted line (see Figure C).

Figure C

Step 4. Empty the contents of the packet into the small container onto the food (see Figure D).

Figure D

Repeat Steps 2 through 4 for each packet of REYATAZ oral powder needed for the total prescribed dose.

Step 5. Use a tablespoon to gently mix the powder and the food together (see Figure E).

Figure E

Steps 6 through 8 must be completed within 1 hour of mixing the medicine.

Step 6. Use the tablespoon or a small spoon to feed the REYATAZ oral powder and food mixture to your child. Look in your child’s mouth to make sure that all of the mixture is swallowed.

Step 7. Add 1 tablespoon more of food to the empty container and gently stir to mix with any contents that may still be in the container.

Step 8. Use the tablespoon or a small spoon to feed your child the mixture, making sure your child has swallowed all of the mixture.

Step 9. Give your child ritonavir as prescribed right after taking REYATAZ oral powder.

Step 10. Wash the container and tablespoon. Allow the container and spoon to dry. Throw away the paper towel and clean the work surface.

Preparing a dose of REYATAZ oral powder mixed with liquid in a small drinking cup:

Before you prepare a dose of REYATAZ oral powder mixed with liquid in a small drinking cup, gather the following supplies:

- paper towel
- spoon
- 30 milliliter (mL) medicine cup (ask your pharmacist for this). See Figure F.
- small drinking cup
- liquid such as milk or water
- the correct number of packets of REYATAZ oral powder needed for the prescribed dose
- a clean pair of scissors

Figure F

Step 1. Using the 30 mL medicine cup, pour at least 30 mL of liquid into the small drinking cup (see Figure G).

Figure G

Step 2. Tap the packet of REYATAZ oral powder to settle the contents to the bottom of the packet (see Figure H).

Figure H

Step 3. Using a clean pair of scissors, cut open the packet on the dotted line (see Figure I).

Figure I

Step 4. Empty the contents of the packet into the small drinking cup (see Figure J).

Figure J

Repeat Steps 2 through 4 for each packet of REYATAZ oral powder needed for the total prescribed dose.

Step 5. Hold the small drinking cup with one hand. With your other hand, use the spoon to gently mix the powder and the liquid (see Figure K).

Figure K

Steps 6 and 7 must be completed within 1 hour of mixing the medicine.

Step 6. Have your child drink all of the mixture in the small drinking cup.

Step 7. To make sure there is no mixture left in the small drinking cup add 15 mL more liquid to the small drinking cup:

- Stir with the spoon.
- Repeat Step 6 above.

If REYATAZ oral powder is mixed with water, your child must eat food right after taking REYATAZ oral powder.

Step 8. Give your child ritonavir as prescribed right after taking REYATAZ oral powder.

Step 9. Wash the small drinking cup, medicine cup, and spoon. Allow the small drinking cup, medicine cup, and spoon to dry. Throw away the paper towel and clean the work surface.

Preparing a dose of REYATAZ oral powder mixed with liquid infant formula using an oral dosing syringe and a small medicine cup:

Before you prepare a dose of REYATAZ oral powder mixed with infant formula using an oral dosing syringe, gather the following supplies:

- paper towel
- small spoon
- 30 milliliter (mL) medicine cup (ask your pharmacist for this). See Figure L.
- 10 mL oral dosing syringe (ask your pharmacist for this). See Figure L.
- infant formula
- the correct number of packets of REYATAZ oral powder needed for the prescribed dose
- a clean pair of scissors

Figure L

Step 1. Prepare the infant formula according to the directions on the infant formula package.

Step 2. Pour 10 mL of infant formula into the medicine cup (see Figure M).

Figure M

Step 3. Tap the packet of REYATAZ oral powder to settle the contents to the bottom of the packet (see Figure N).

Figure N

Step 4. Using a clean pair of scissors, cut open the packet on the dotted line (see Figure O).

Figure O

Step 5. Empty the contents of the packet into the medicine cup (see Figure P).

Figure P

Repeat Steps 3 through 5 for each packet of REYATAZ oral powder needed for the total prescribed dose.

Step 6. Hold the medicine cup with one hand. With your other hand, use the small spoon to gently mix the powder and the infant formula (see Figure Q).

Figure Q

Steps 7 through 9 must be completed within 1 hour of mixing the medicine.

Step 7. Draw up the powder and infant formula mixture into the oral dosing syringe as follows:

- Check that the plunger is completely pushed into barrel of the syringe (see Figure R).

Figure R

- Place the tip of the syringe into the powder and infant formula mixture in the medicine cup (see Figure S).

Figure S

- Slowly pull back on the plunger and draw up 10 mL of the mixture (see Figure T).

Figure T

Step 8. Place the tip of the oral dosing syringe in your baby’s mouth along the inner cheek on either the right or left side (see Figure U). Slowly push on the plunger to give your baby all of the REYATAZ oral powder and infant formula mixture.

- Draw up any remaining mixture with the oral dosing syringe and repeat until all of the mixture has been given to the baby.

Figure U

Step 9. To make sure there is no mixture left in the medicine cup or syringe:

- Repeat Step 1 above to add 10 mL more infant formula to the medicine cup.
- Stir with a small spoon.
- Then repeat Steps 7 through 8 above.

To make sure that your baby gets all of the medicine, do not give REYATAZ oral powder in a baby bottle.

Step 10. Give your baby ritonavir as prescribed right after taking REYATAZ oral powder.

Step 11. Remove the plunger from the oral dosing syringe. Wash the medicine cup, spoon, and oral dosing syringe. Allow the medicine cup, spoon, and oral dosing syringe to dry. Throw away the paper towel and clean the work surface.

How should I store REYATAZ oral powder?

- Store REYATAZ oral powder at a temperature of 68°F to 86°F (20°C to 30°C).
- Store REYATAZ oral powder in the original packet. Do not open until ready to use.
- After REYATAZ oral powder is mixed with food or liquid, it may be kept at a temperature of 68°F to 86°F (20°C to 30°C) for up to 1 hour. Take REYATAZ oral powder within 1 hour after mixing with food or liquid.
Keep REYATAZ oral powder and all medicines out of the reach of children.
This Instructions for Use has been approved by the U.S. Food and Drug Administration.

Distributed by:
Bristol-Myers Squibb Company
Princeton, NJ 08543 USA

[print code] | Revised: September 2020

REYATAZ 150 mg Capsules Representative Packaging

See HOW SUPPLIED section for a complete list of available packages of REYATAZ.

NDC 0003-3624-12
Bristol Myers Squibb
60 Capsules
REYATAZ®
(atazanavir) capsules
150 mg
Rx only

Note to pharmacist: Do not cover ALERT box with pharmacy label.
ALERT: Find out about medicines that should NOT be taken with REYATAZ®

REYATAZ 200 mg Capsules Representative Packaging

NDC 0003-3631-12
Bristol Myers Squibb
60 Capsules
REYATAZ®
(atazanavir) capsules
200 mg
Rx only
Note to pharmacist: Do not cover ALERT box with pharmacy label.
ALERT: Find out about medicines that should NOT be taken with REYATAZ®

REYATAZ 300 mg Capsules Representative Packaging

NDC 0003-3622-12
Bristol Myers Squibb
30 Capsules
REYATAZ®
(atazanavir) capsules
300 mg
Rx only
Note to pharmacist: Do not cover ALERT box with pharmacy label.
ALERT: Find out about medicines that should NOT be taken with REYATAZ®

REYATAZ 50 mg Oral Powder Representative Packaging

NDC 0003-3638-10
Bristol Myers Squibb
One Packet
REYATAZ®
(atazanavir) oral powder
50 mg
Rx only
For patients who are at least 3 months of age and weigh at least 5 kg.
Mix with food or beverage before taking this medicine. See Instructions for Use.
Note to pharmacist: Do not cover ALERT box with pharmacy label.
ALERT: Find out about medicines that should NOT be taken with REYATAZ®
Each packet contains 50 mg of atazanavir as atazanavir sulfate in 1.5 g of powder.
Phenylketonurics: Contains phenylalanine 35 mg per 1.5 g of powder (per packet).
Keep out of the reach of children.